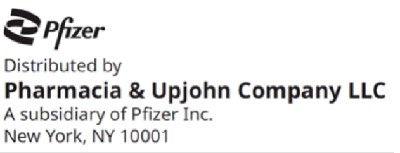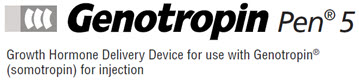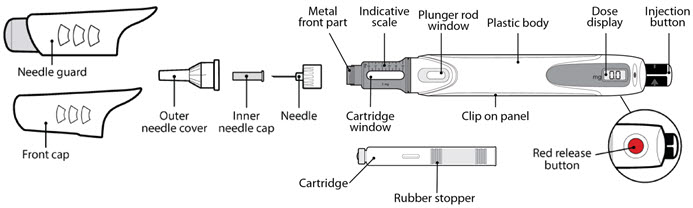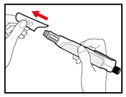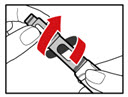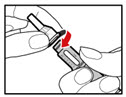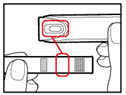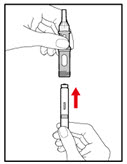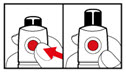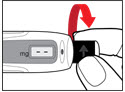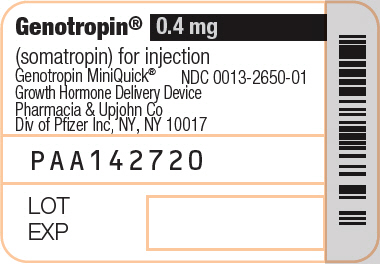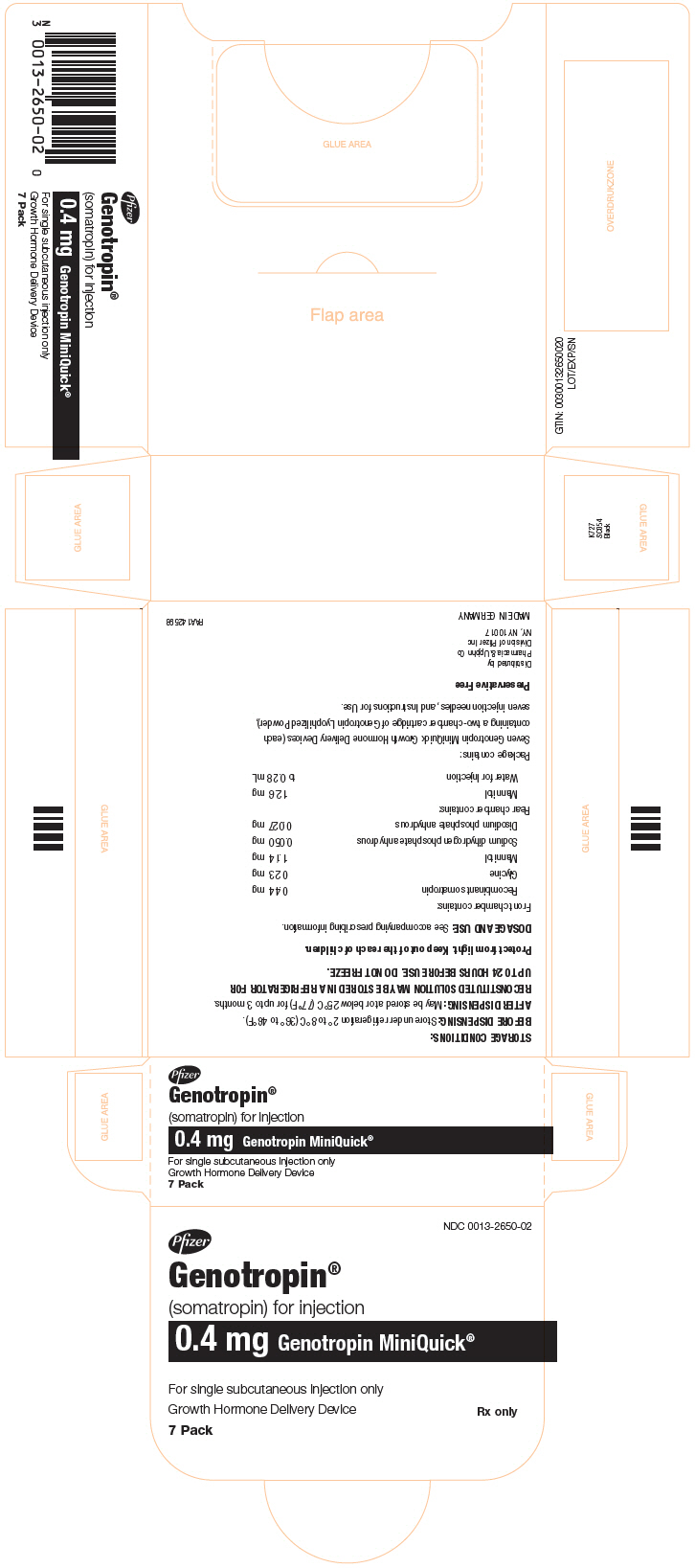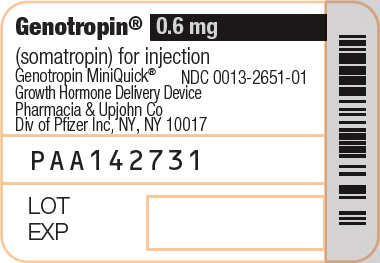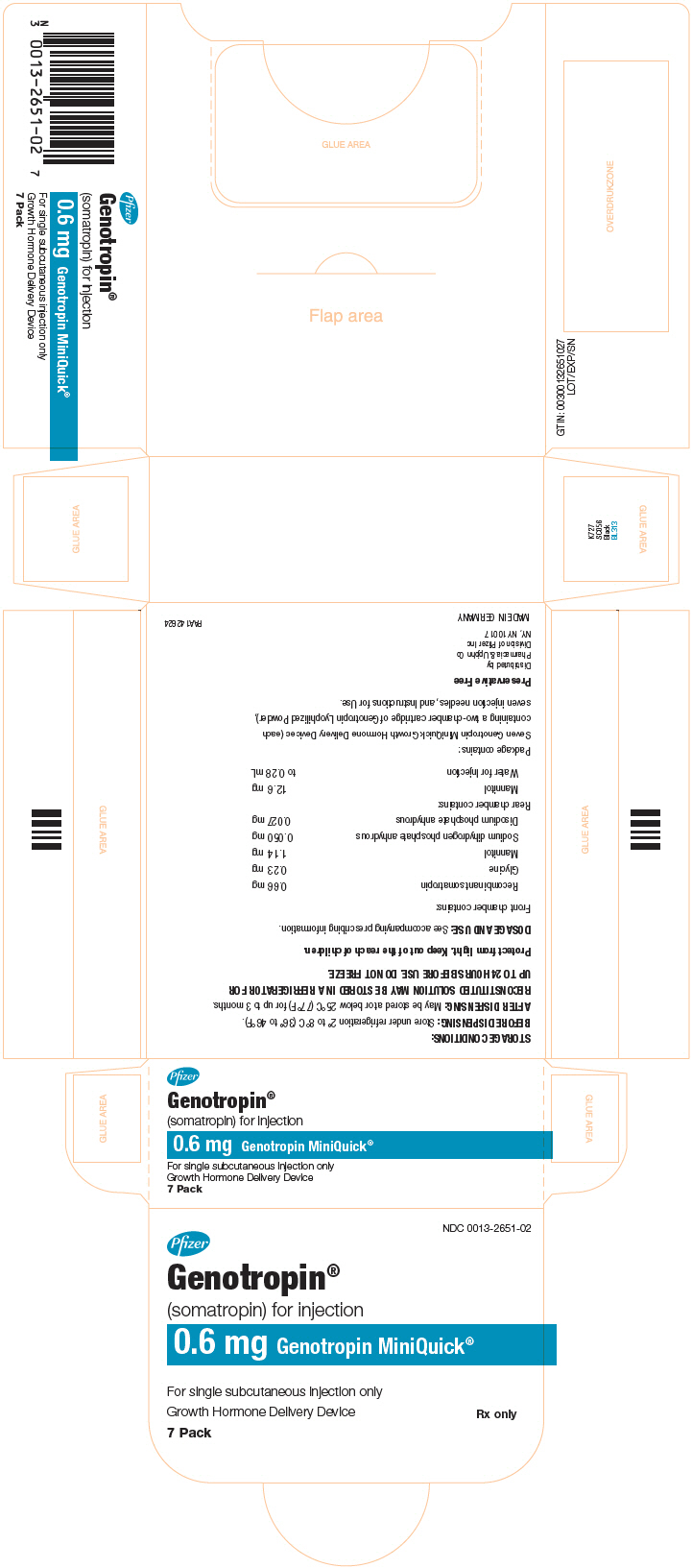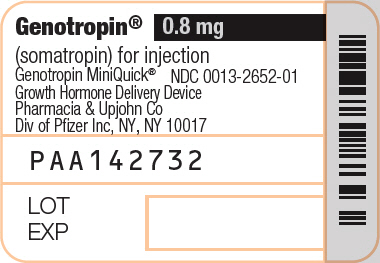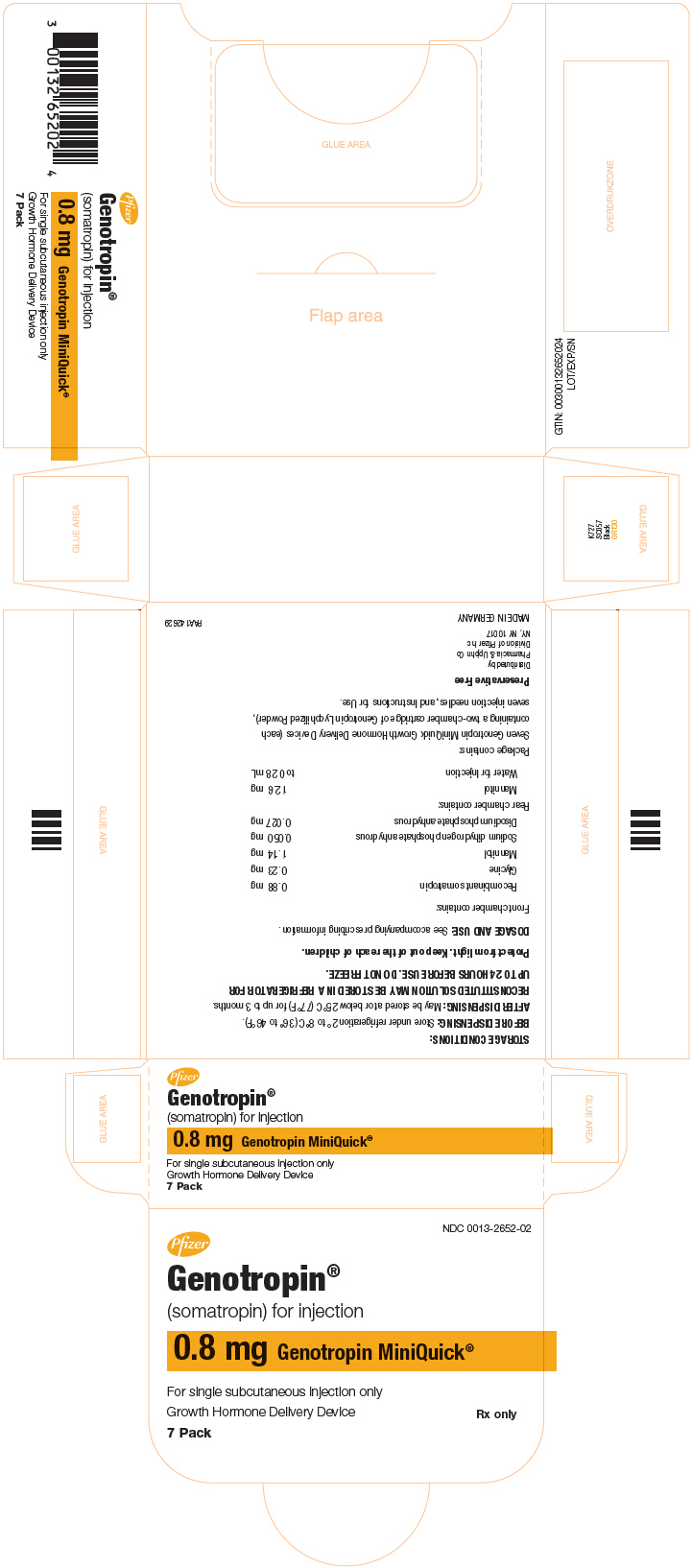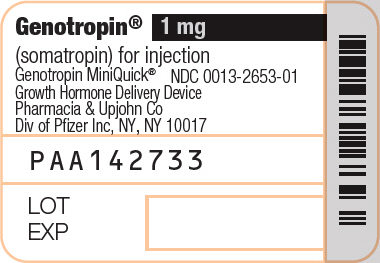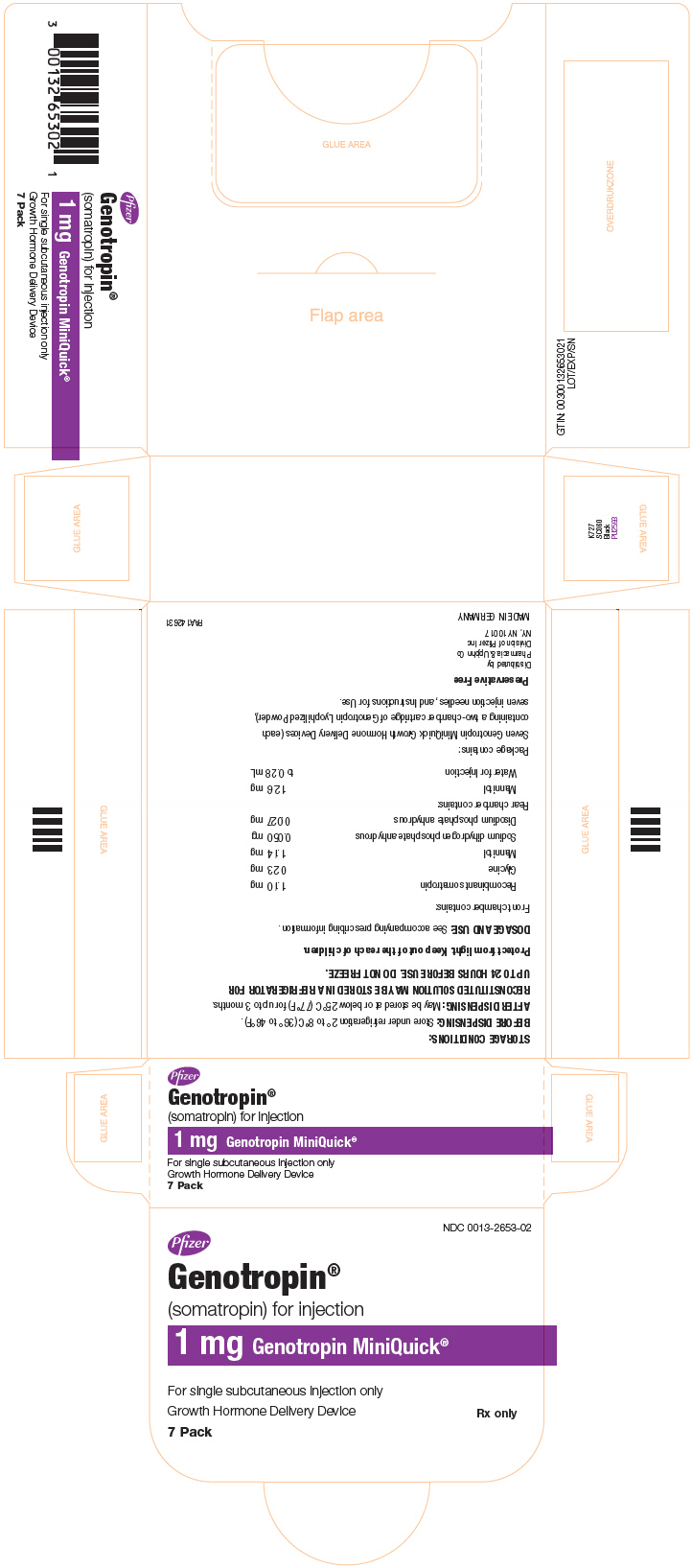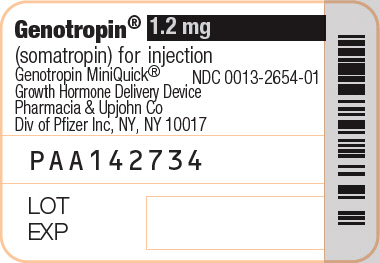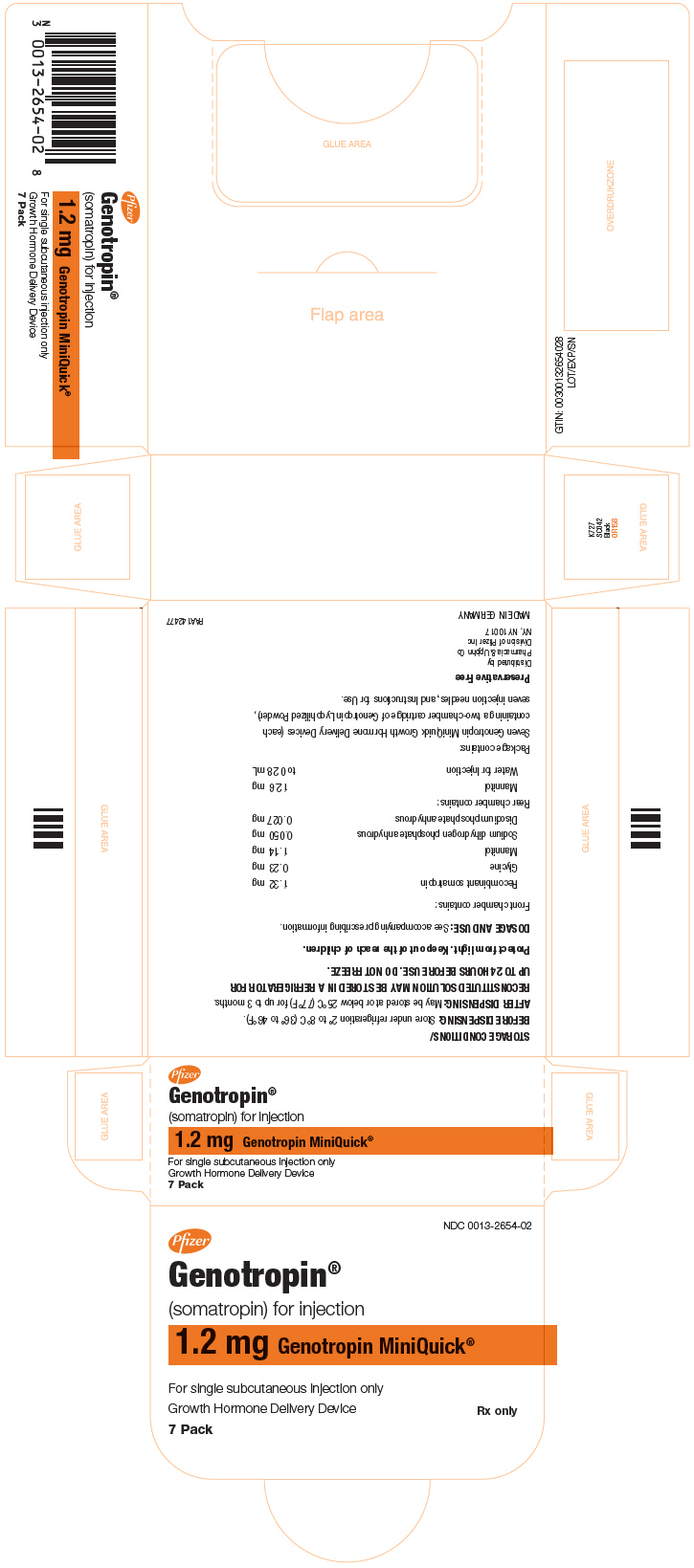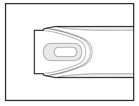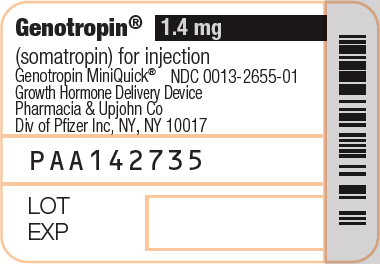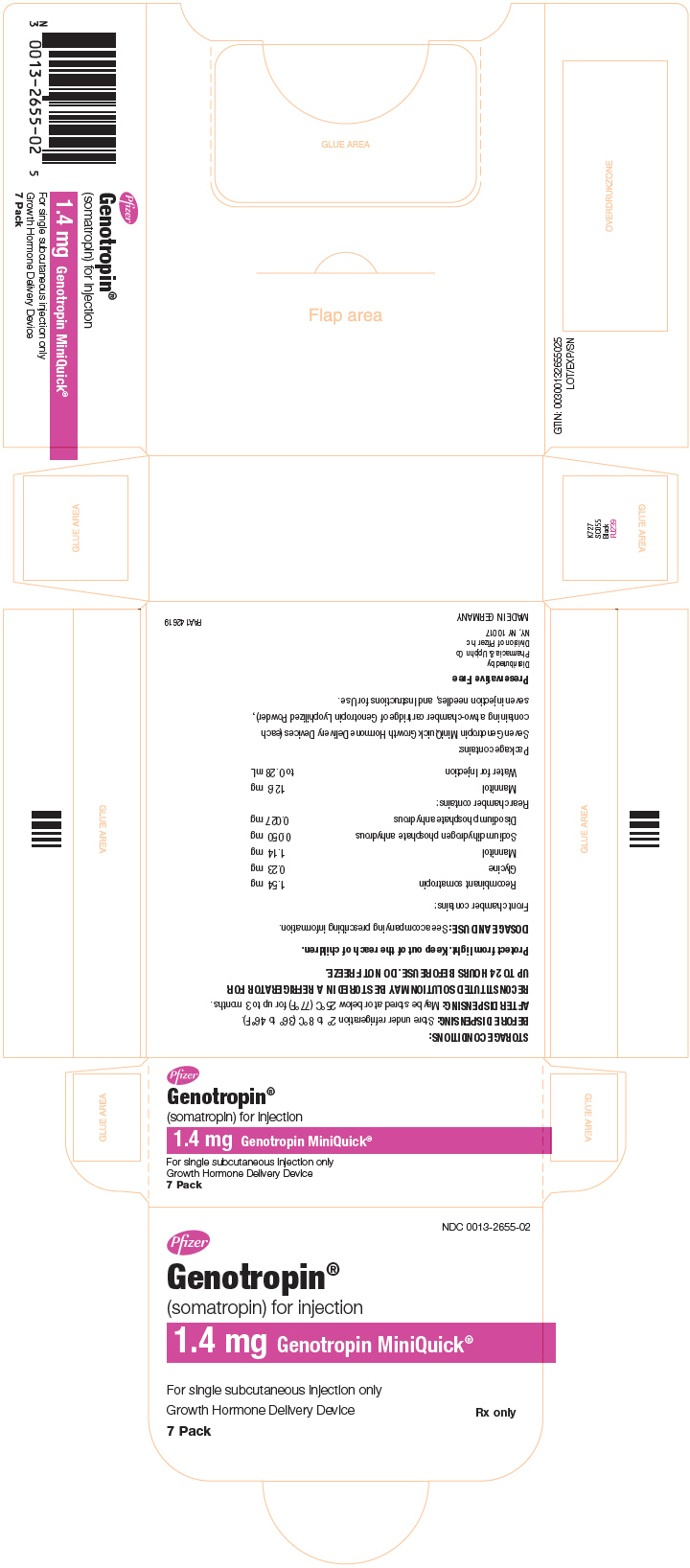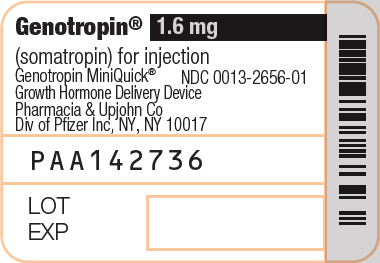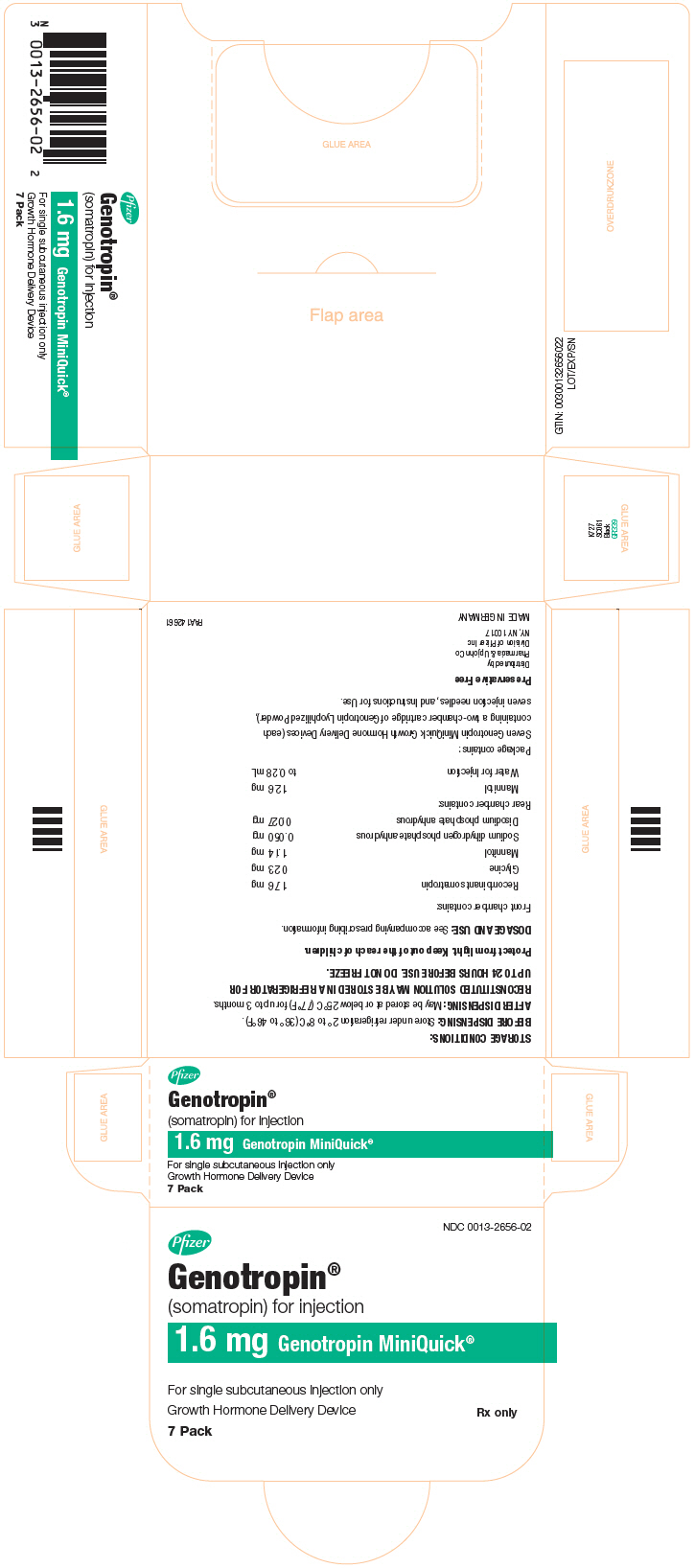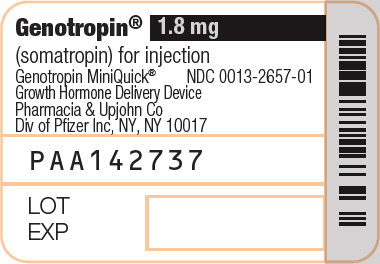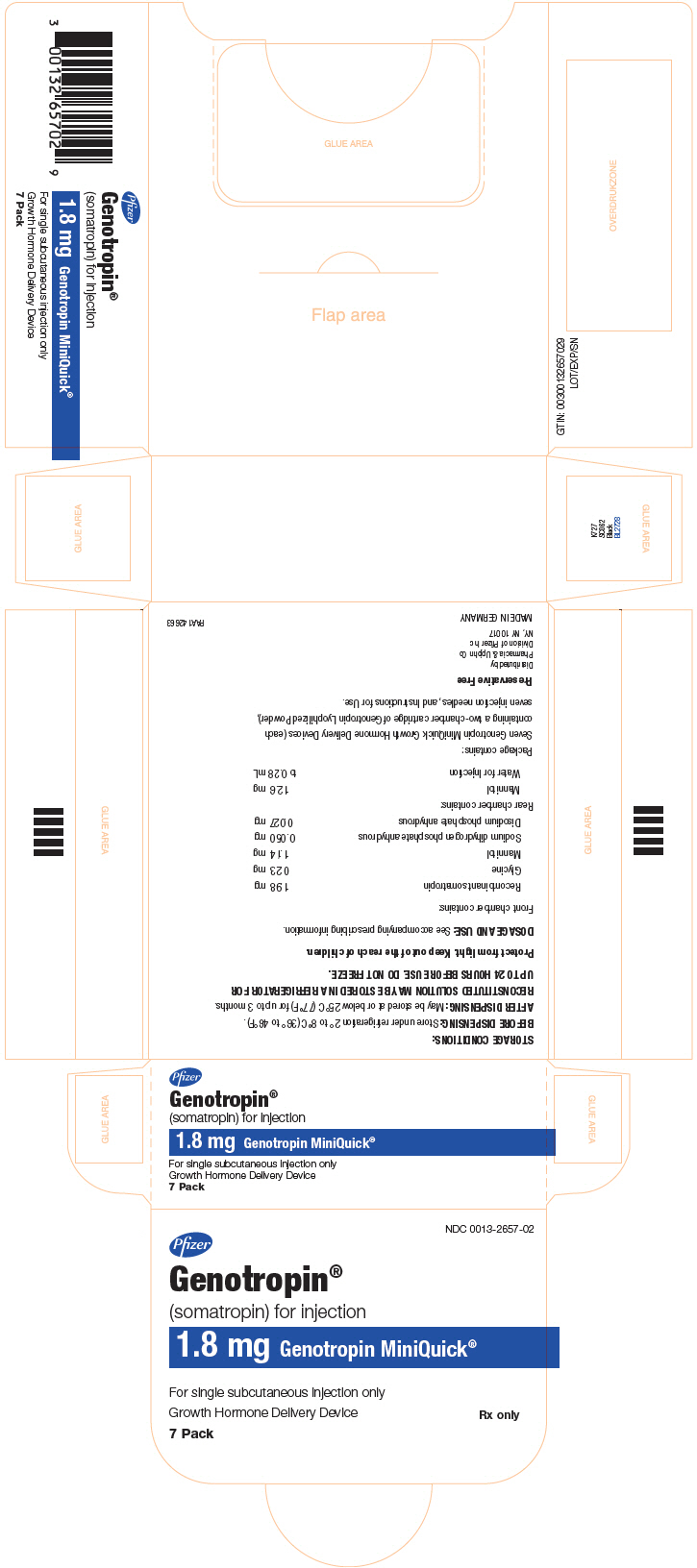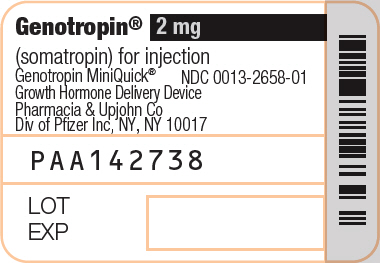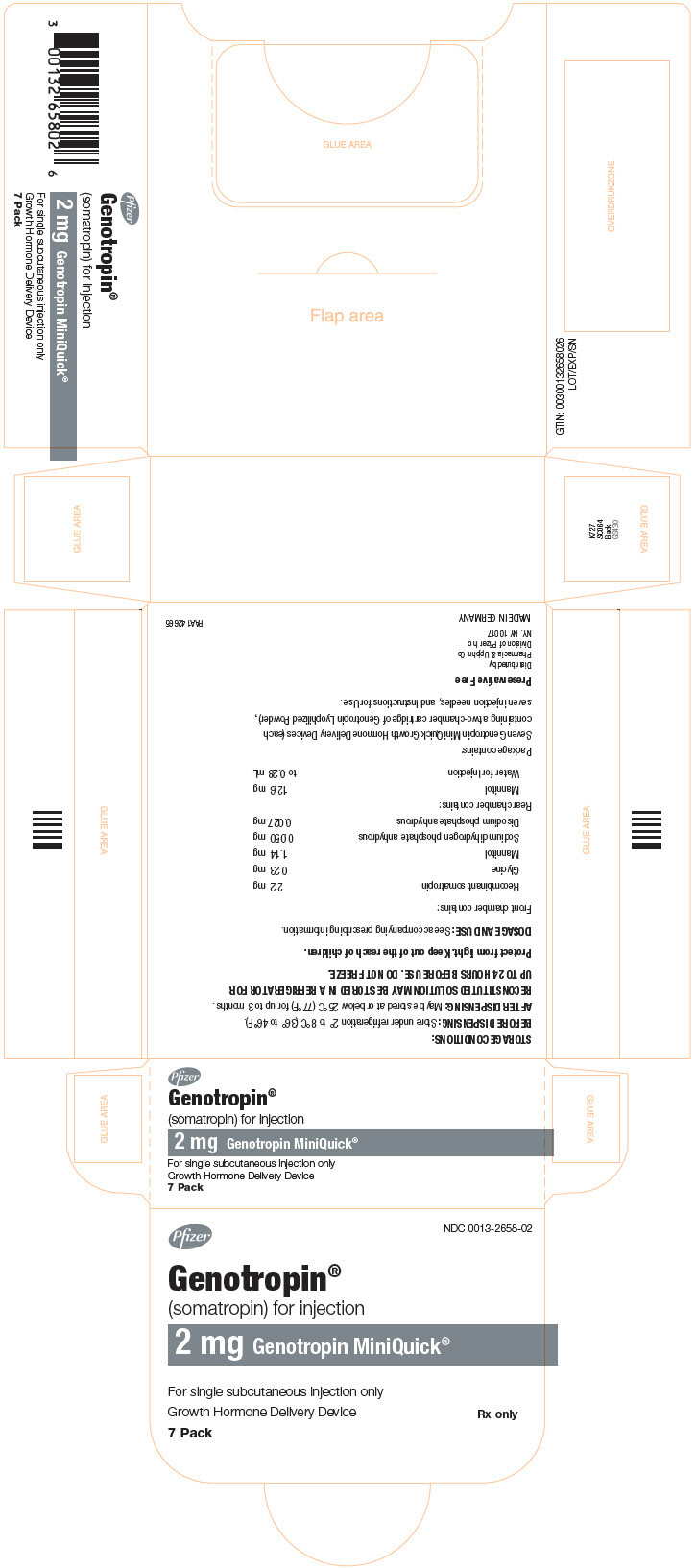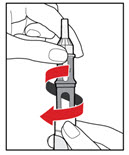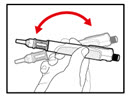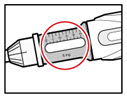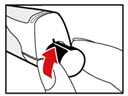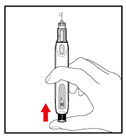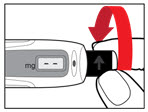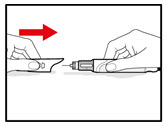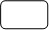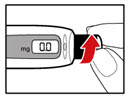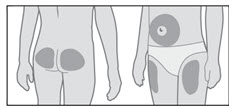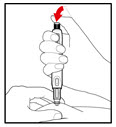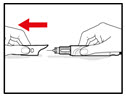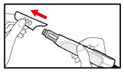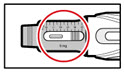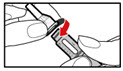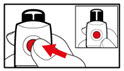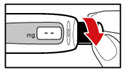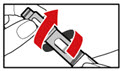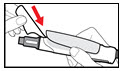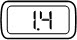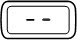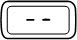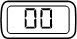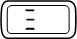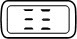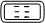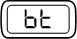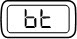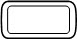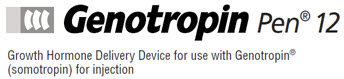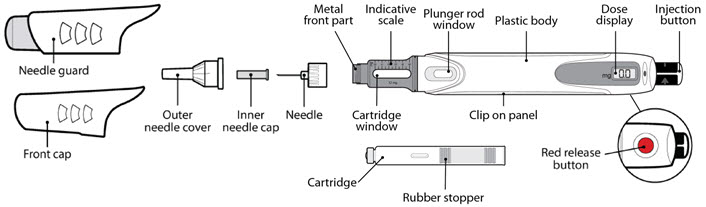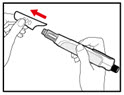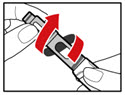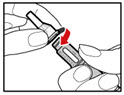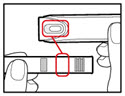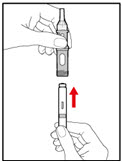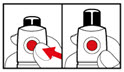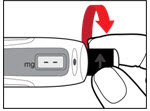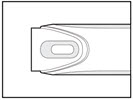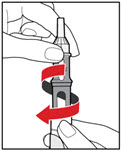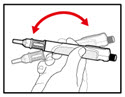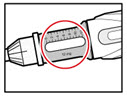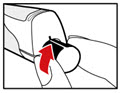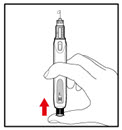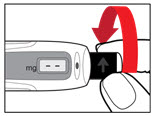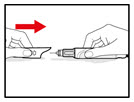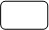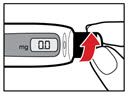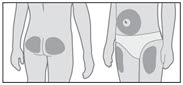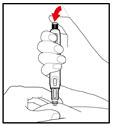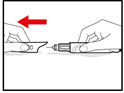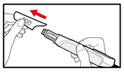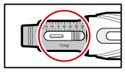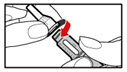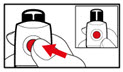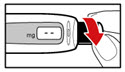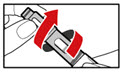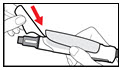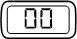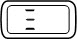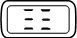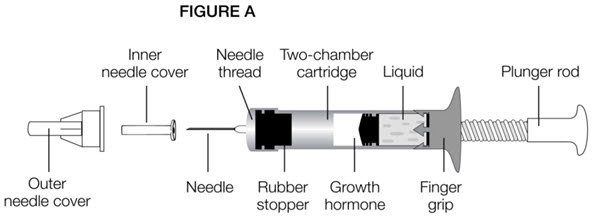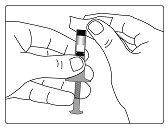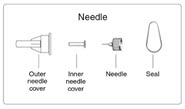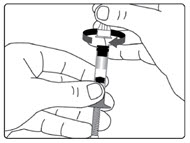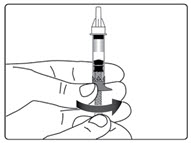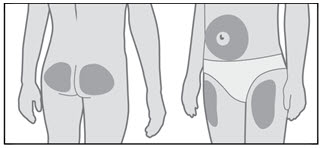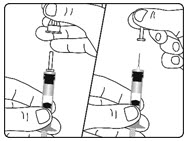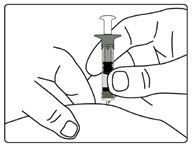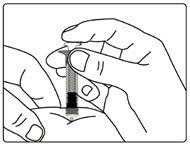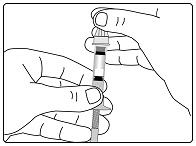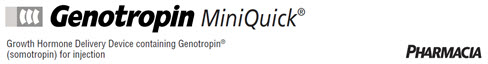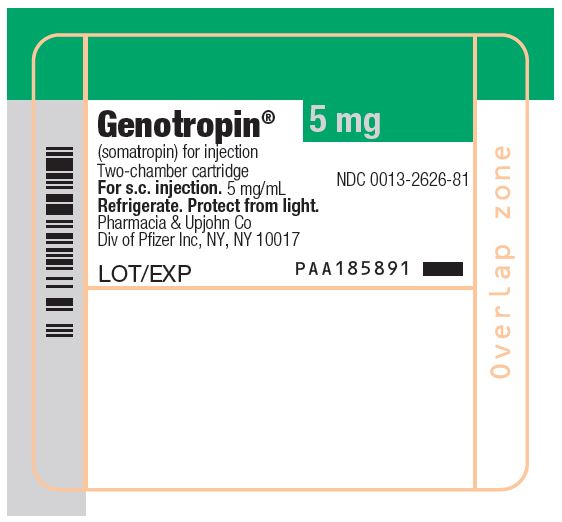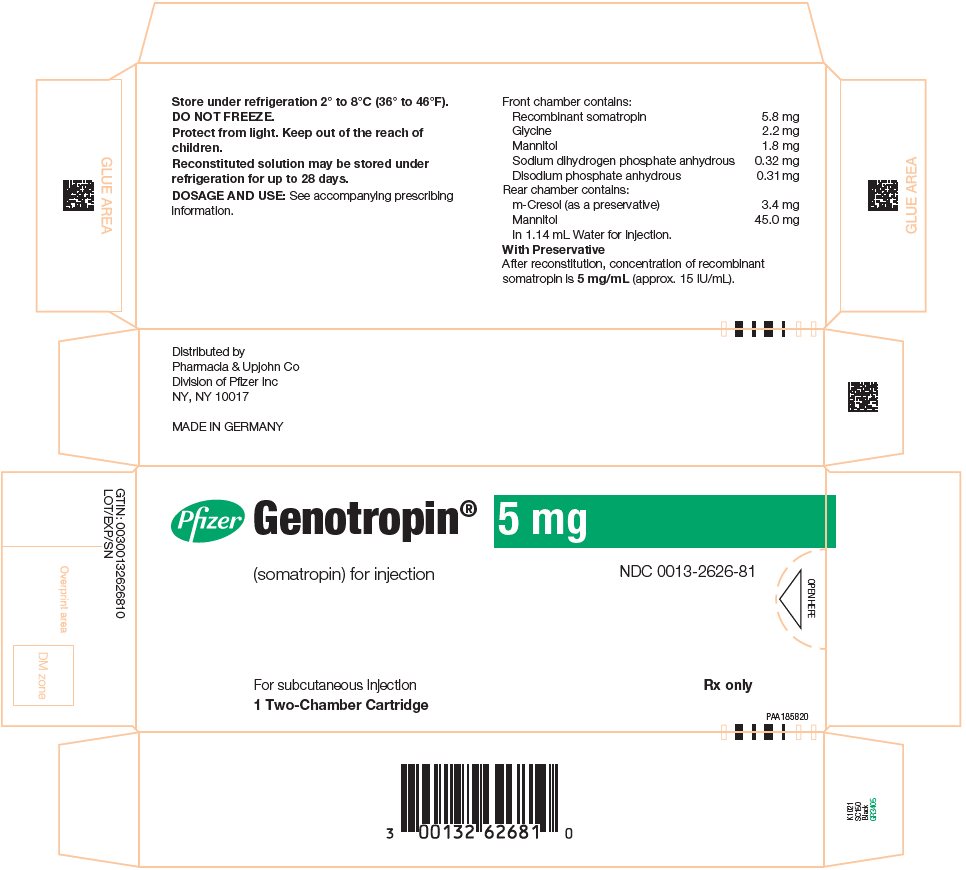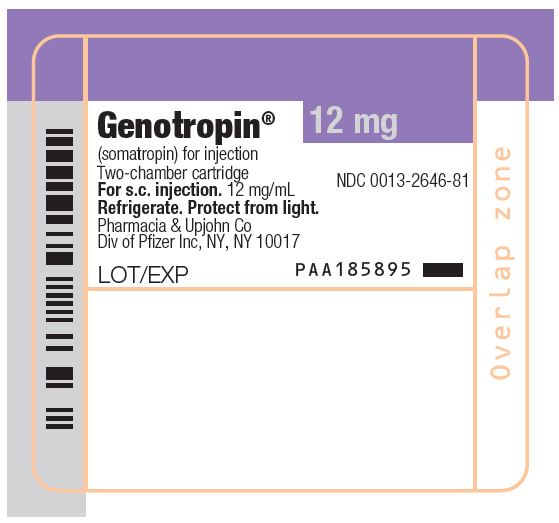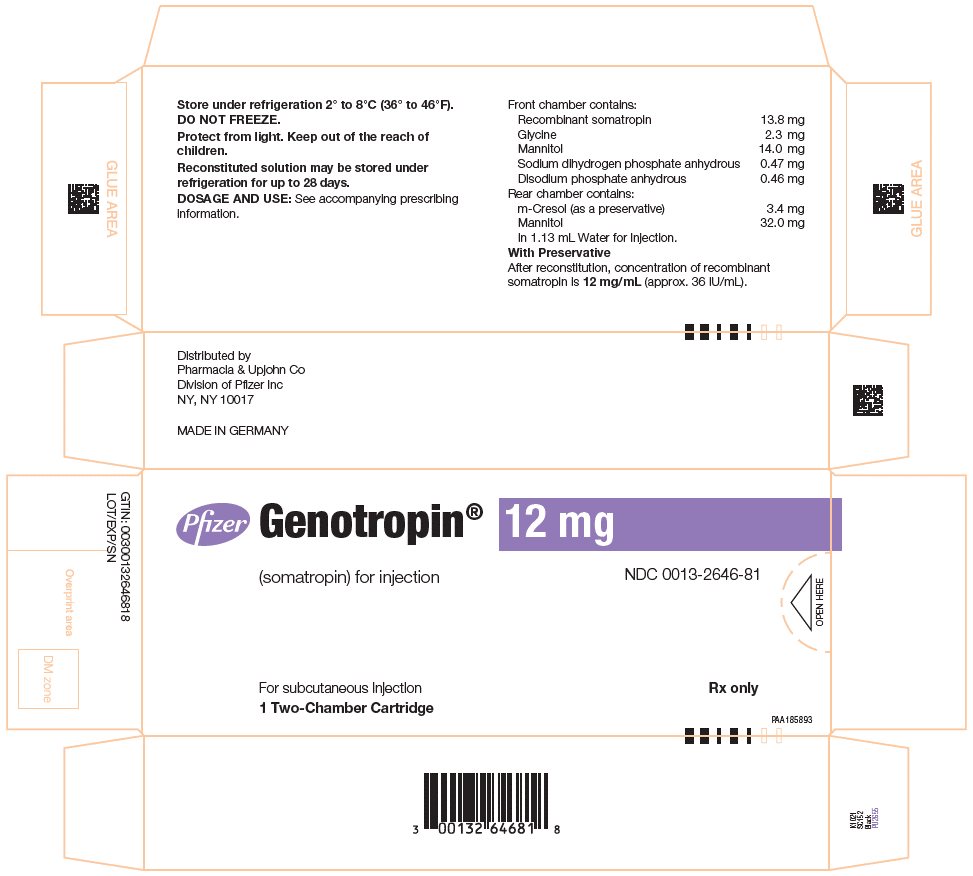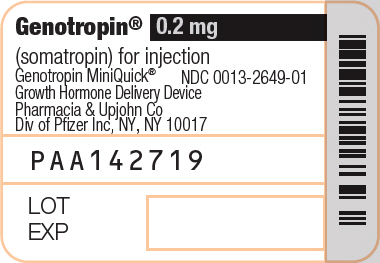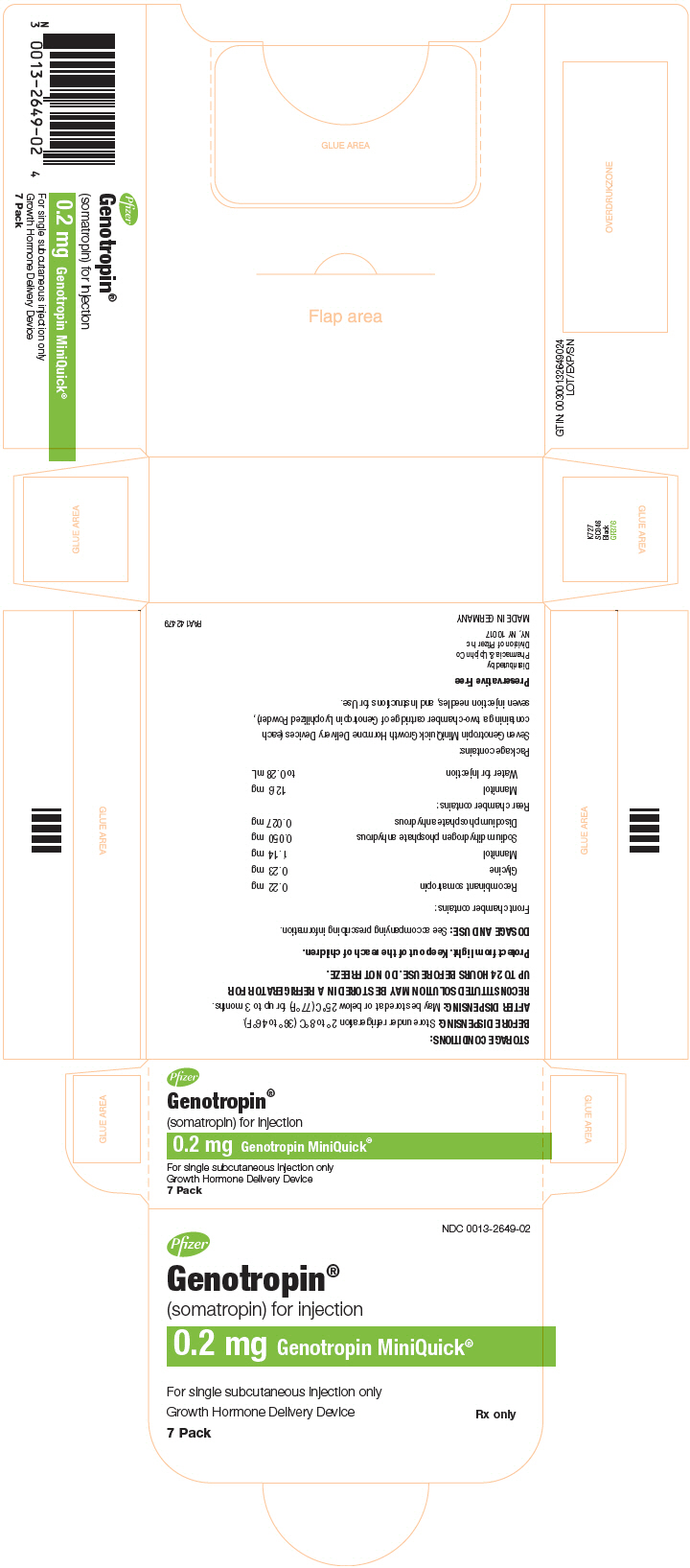 DRUG LABEL: GENOTROPIN
NDC: 0013-2626 | Form: KIT | Route: SUBCUTANEOUS
Manufacturer: Pfizer Laboratories Div Pfizer Inc
Category: prescription | Type: HUMAN PRESCRIPTION DRUG LABEL
Date: 20250716

ACTIVE INGREDIENTS: SOMATROPIN 5 mg/1 mL
INACTIVE INGREDIENTS: GLYCINE; MANNITOL; SODIUM PHOSPHATE, MONOBASIC, ANHYDROUS; WATER; MANNITOL 45 mg/1.14 mL

HIGHLIGHTS OF PRESCRIBING INFORMATION

These highlights do not include all the information needed to use GENOTROPIN safely and effectively. See full prescribing information for GENOTROPIN
GENOTROPIN® (somatropin) for injection, for subcutaneous use
Initial U.S. Approval: 1987

RECENT MAJOR CHANGES

Warnings and Precautions, Slipped Capital Femoral Epiphysis in Pediatric Patients (5.10) | 07/2025

1 INDICATIONS AND USAGE

GENOTROPIN is a recombinant human growth hormone indicated for:

- Pediatric: Treatment of children with growth failure due to growth hormone deficiency (GHD), Prader-Willi syndrome, Small for Gestational Age, Turner syndrome, and Idiopathic Short Stature (1.1)
- Adult: Treatment of adults with either adult onset or childhood onset GHD (1.2)

2 DOSAGE AND ADMINISTRATION

GENOTROPIN should be administered subcutaneously (2)

- Pediatric GHD: 0.16 to 0.24 mg/kg/week (2.1)
- Prader-Willi Syndrome: 0.24 mg/kg/week (2.1)
- Small for Gestational Age: Up to 0.48 mg/kg/week (2.1)
- Turner Syndrome: 0.33 mg/kg/week (2.1)
- Idiopathic Short Stature: up to 0.47 mg/kg/week (2.1)
- Adult GHD: Either a non-weight based or a weight based dosing regimen may be followed, with doses adjusted based on treatment response and IGF-I concentrations (2.2)
- Non-weight based dosing: A starting dose of approximately 0.2 mg/day (range, 0.15–0.30 mg/day) may be used without consideration of body weight, and increased gradually every 1–2 months by increments of approximately 0.1–0.2 mg/day. (2.2)
- Weight based dosing: The recommended initial dose is not more than 0.04 mg/kg/week; the dose may be increased as tolerated to not more than 0.08 mg/kg/week at 4–8 week intervals. (2.2)
- GENOTROPIN cartridges are color-coded to correspond to a specific GENOTROPIN PEN delivery device (2.3)
- Injection sites should always be rotated to avoid lipoatrophy (2.3)

3 DOSAGE FORMS AND STRENGTHS

For injection: 5 mg or 12 mg lyophilized powder in a single‑patient‑use two‑chamber cartridge (3)

For injection: 0.2 mg, 0.4 mg, 0.6 mg, 0.8 mg, 1 mg, 1.2 mg, 1.4 mg, 1.6 mg, 1.8 mg, or 2 mg lyophilized powder in a single-dose Growth Hormone Delivery Device containing a two-chamber cartridge (GENOTROPIN MINIQUICK) (3)

4 CONTRAINDICATIONS

- Acute Critical Illness (4)
- Children with Prader-Willi syndrome who are severely obese or have severe respiratory impairment – reports of sudden death (4)
- Active Malignancy (4)
- Hypersensitivity to somatropin or excipients (4)
- Active Proliferative or Severe Non-Proliferative Diabetic Retinopathy (4)
- Children with closed epiphyses (4)

5 WARNINGS AND PRECAUTIONS

- Acute Critical Illness: Potential benefit of treatment continuation should be weighed against the potential risk (5.1)
- Prader-Willi Syndrome in Children: Evaluate for signs of upper airway obstruction and sleep apnea before initiation of treatment
  Discontinue treatment if these signs occur (5.2)
- Neoplasm: Monitor patients with preexisting tumors for progression or recurrence. Increased risk of a second neoplasm in childhood cancer survivors treated with somatropin in particular meningiomas in patients treated with radiation to the head for their first neoplasm (5.3)
- Impaired Glucose Tolerance and Diabetes Mellitus: May be unmasked
  Periodically monitor glucose levels in all patients. Doses of concurrent antihyperglycemic drugs in diabetics may require adjustment (5.4)
- Intracranial Hypertension: Exclude preexisting papilledema. May develop and is usually reversible after discontinuation or dose reduction (5.5)
- Hypersensitivity: Serious hypersensitivity reactions may occur. In the event of an allergic reaction, seek prompt medical attention (5.6)
- Fluid Retention (i.e., edema, arthralgia, carpal tunnel syndrome – especially in adults): May occur frequently. Reduce dose as necessary (5.7)
- Hypoadrenalism: Monitor patients for reduced serum cortisol levels and/or need for glucocorticoid dose increases in those with known hypoadrenalism (5.8)
- Hypothyroidism: May first become evident or worsen. Monitor thyroid function periodically (5.9)
- Slipped Capital Femoral Epiphysis: May develop. Evaluate children with the onset of a limp or hip/knee pain (5.10)
- Progression of Preexisting Scoliosis: Monitor any child with scoliosis for progression of the curve (5.11)
- Pancreatitis: Consider pancreatitis in patients with persistent severe abdominal pain (5.15)

6 ADVERSE REACTIONS

Other common somatropin-related adverse reactions include injection site reactions/rashes and lipoatrophy (6.1) and headaches (6.2).

To report SUSPECTED ADVERSE REACTIONS, contact Pfizer Inc. at 1-800-438-1985 or FDA at 1-800-FDA-1088 or www.fda.gov/medwatch.

7 DRUG INTERACTIONS

Inhibition of 11ß-Hydroxysteroid Dehydrogenase Type 1: May require the initiation of glucocorticoid replacement therapy. Patients treated with glucocorticoid replacement for previously diagnosed hypoadrenalism may require an increase in their maintenance doses (7.1, 7.2).

- Glucocorticoid Replacement: Should be carefully adjusted (7.2)
- Cytochrome P450-Metabolized Drugs: Monitor carefully if used with somatropin (7.3)
- Oral Estrogen: Larger doses of somatropin may be required in women (7.4)
- Insulin and/or Oral/Injectable Hypoglycemic Agents: May require adjustment (7.5)

FULL PRESCRIBING INFORMATION

1 INDICATIONS AND USAGE

1.1 Pediatric Patients

GENOTROPIN is indicated for the treatment of pediatric patients who have growth failure due to an inadequate secretion of endogenous growth hormone.

GENOTROPIN is indicated for the treatment of pediatric patients who have growth failure due to Prader-Willi syndrome (PWS). The diagnosis of PWS should be confirmed by appropriate genetic testing [see Contraindications (4)].

GENOTROPIN is indicated for the treatment of growth failure in pediatric patients born small for gestational age (SGA) who fail to manifest catch-up growth by age 2 years.

GENOTROPIN is indicated for the treatment of growth failure associated with Turner syndrome.

GENOTROPIN is indicated for the treatment of idiopathic short stature (ISS), also called non-growth hormone-deficient short stature, defined by height standard deviation score (SDS) ≤-2.25, and associated with growth rates unlikely to permit attainment of adult height in the normal range, in pediatric patients whose epiphyses are not closed and for whom diagnostic evaluation excludes other causes associated with short stature that should be observed or treated by other means.

1.2 Adult Patients

GENOTROPIN is indicated for replacement of endogenous growth hormone in adults with growth hormone deficiency who meet either of the following two criteria:

Adult Onset (AO): Patients who have growth hormone deficiency, either alone or associated with multiple hormone deficiencies (hypopituitarism), as a result of pituitary disease, hypothalamic disease, surgery, radiation therapy, or trauma; or

Childhood Onset (CO): Patients who were growth hormone deficient during childhood as a result of congenital, genetic, acquired, or idiopathic causes.

Patients who were treated with somatropin for growth hormone deficiency in childhood and whose epiphyses are closed should be reevaluated before continuation of somatropin therapy at the reduced dose level recommended for growth hormone deficient adults. According to current standards, confirmation of the diagnosis of adult growth hormone deficiency in both groups involves an appropriate growth hormone provocative test with two exceptions: (1) patients with multiple other pituitary hormone deficiencies due to organic disease; and (2) patients with congenital/genetic growth hormone deficiency.

2 DOSAGE AND ADMINISTRATION

The weekly dose should be divided into 6 or 7 subcutaneous injections. GENOTROPIN must not be injected intravenously.

Therapy with GENOTROPIN should be supervised by a physician who is experienced in the diagnosis and management of pediatric patients with growth failure associated with growth hormone deficiency (GHD), Prader-Willi syndrome (PWS), Turner syndrome (TS), those who were born small for gestational age (SGA) or Idiopathic Short Stature (ISS), and adult patients with either childhood onset or adult onset GHD.

2.1 Dosing of Pediatric Patients

General Pediatric Dosing Information

The GENOTROPIN dosage and administration schedule should be individualized based on the growth response of each patient.

Response to somatropin therapy in pediatric patients tends to decrease with time. However, in pediatric patients, the failure to increase growth rate, particularly during the first year of therapy, indicates the need for close assessment of compliance and evaluation for other causes of growth failure, such as hypothyroidism, undernutrition, advanced bone age and antibodies to recombinant human GH (rhGH).

Treatment with GENOTROPIN for short stature should be discontinued when the epiphyses are fused.

Pediatric Growth Hormone Deficiency (GHD)

Generally, a dose of 0.16 to 0.24 mg/kg body weight/week is recommended.

Prader-Willi Syndrome

Generally, a dose of 0.24 mg/kg body weight/week is recommended.

Turner Syndrome

Generally, a dose of 0.33 mg/kg body weight/week is recommended.

Idiopathic Short Stature

Generally, a dose up to 0.47 mg/kg body weight/week is recommended.

Small for Gestational Age [Recent literature has recommended initial treatment with larger doses of somatropin (e.g., 0.48 mg/kg/week), especially in very short children (i.e., height SDS <–3), and/or older/ pubertal children, and that a reduction in dosage (e.g., gradually towards 0.24 mg/kg/week) should be considered if substantial catch-up growth is observed during the first few years of therapy. On the other hand, in younger SGA children (e.g., approximately <4 years) (who respond the best in general) with less severe short stature (i.e., baseline height SDS values between -2 and -3), consideration should be given to initiating treatment at a lower dose (e.g., 0.24 mg/kg/week), and titrating the dose as needed over time. In all children, clinicians should carefully monitor the growth response, and adjust the somatropin dose as necessary.]

Generally, a dose of up to 0.48 mg/kg body weight/week is recommended.

2.2 Dosing of Adult Patients

Adult Growth Hormone Deficiency (GHD)

Either of two approaches to GENOTROPIN dosing may be followed: a non-weight based regimen or a weight based regimen.

Non-weight based — based on published consensus guidelines, a starting dose of approximately 0.2 mg/day (range, 0.15–0.30 mg/day) may be used without consideration of body weight. This dose can be increased gradually every 1–2 months by increments of approximately 0.1–0.2 mg/day, according to individual patient requirements based on the clinical response and serum insulin-like growth factor I (IGF-I) concentrations. The dose should be decreased as necessary on the basis of adverse events and/or serum IGF-I concentrations above the age- and gender-specific normal range. Maintenance dosages vary considerably from person to person, and between male and female patients.

Weight based — based on the dosing regimen used in the original adult GHD registration trials, the recommended dosage at the start of treatment is not more than 0.04 mg/kg/week. The dose may be increased according to individual patient requirements to not more than 0.08 mg/kg/week at 4–8 week intervals. Clinical response, side effects, and determination of age- and gender-adjusted serum IGF-I concentrations should be used as guidance in dose titration.

A lower starting dose and smaller dose increments should be considered for older patients, who are more prone to the adverse effects of somatropin than younger individuals. In addition, obese individuals are more likely to manifest adverse effects when treated with a weight-based regimen. In order to reach the defined treatment goal, estrogen-replete women may need higher doses than men. Oral estrogen administration may increase the dose requirements in women.

2.3 Preparation and Administration

The GENOTROPIN 5 and 12 mg cartridges are color-coded to help ensure proper use with the GENOTROPIN PEN delivery device. The 5 mg cartridge has a green tip to match the green pen window on the Pen 5, while the 12 mg cartridge has a purple tip to match the purple pen window on the Pen 12.

Parenteral drug products should always be inspected visually for particulate matter and discoloration prior to administration, whenever solution and container permit. GENOTROPIN MUST NOT BE INJECTED if the solution is cloudy or contains particulate matter. Use it only if it is clear and colorless.

GENOTROPIN may be given in the thigh, buttocks, or abdomen; the site of SC injections should be rotated daily to help prevent lipoatrophy.

3 DOSAGE FORMS AND STRENGTHS

GENOTROPIN is a white, lyophilized powder available as:

- For injection: 5 mg or 12 mg in a single-patient-use two-chamber cartridge
- For injection: 0.2 mg, 0.4 mg, 0.6 mg, 0.8 mg, 1 mg, 1.2 mg, 1.4 mg, 1.6 mg, 1.8 mg, or 2 mg in a single‑dose Growth Hormone Delivery Device containing a two-chamber cartridge (GENOTROPIN MINIQUICK)

4 CONTRAINDICATIONS

GENOTROPIN is contraindicated in patients with:

• Acute Critical Illness

Treatment with pharmacologic amounts of somatropin is contraindicated in patients with acute critical illness due to complications following open heart surgery, abdominal surgery or multiple accidental trauma, or those with acute respiratory failure [see Warnings and Precautions (5.1)].

• Prader-Willi Syndrome in Children

Somatropin is contraindicated in patients with Prader-Willi syndrome who are severely obese, have a history of upper airway obstruction or sleep apnea, or have severe respiratory impairment. There have been reports of sudden death when somatropin was used in such patients [see Warnings and Precautions (5.2)].

• Active Malignancy

In general, somatropin is contraindicated in the presence of active malignancy. Any preexisting malignancy should be inactive and its treatment complete prior to instituting therapy with somatropin. Somatropin should be discontinued if there is evidence of recurrent activity. Since growth hormone deficiency may be an early sign of the presence of a pituitary tumor (or, rarely, other brain tumors), the presence of such tumors should be ruled out prior to initiation of treatment. Somatropin should not be used in patients with any evidence of progression or recurrence of an underlying intracranial tumor.

• Hypersensitivity

GENOTROPIN is contraindicated in patients with a known hypersensitivity to somatropin or any of its excipients. The 5 mg and 12 mg presentations of GENOTROPIN lyophilized powder contain m-cresol as a preservative. Systemic hypersensitivity reactions have been reported with postmarketing use of somatropins [see Warnings and Precautions (5.6)].

• Diabetic Retinopathy

Somatropin is contraindicated in patients with active proliferative or severe non-proliferative diabetic retinopathy.

• Closed Epiphyses

Somatropin should not be used for growth promotion in pediatric patients with closed epiphyses.

5 WARNINGS AND PRECAUTIONS

5.1 Acute Critical Illness

Increased mortality in patients with acute critical illness due to complications following open heart surgery, abdominal surgery or multiple accidental trauma, or those with acute respiratory failure has been reported after treatment with pharmacologic amounts of somatropin [see Contraindications (4)]. Two placebo-controlled clinical trials in non-growth hormone deficient adult patients (n=522) with these conditions in intensive care units revealed a significant increase in mortality (42% vs. 19%) among somatropin-treated patients (doses 5.3–8 mg/day) compared to those receiving placebo. The safety of continuing somatropin treatment in patients receiving replacement doses for approved indications who concurrently develop these illnesses has not been established. Therefore, the potential benefit of treatment continuation with somatropin in patients having acute critical illnesses should be weighed against the potential risk.

5.2 Prader-Willi Syndrome in Children

There have been reports of fatalities after initiating therapy with somatropin in pediatric patients with Prader-Willi syndrome who had one or more of the following risk factors: severe obesity, history of upper airway obstruction or sleep apnea, or unidentified respiratory infection. Male patients with one or more of these factors may be at greater risk than females. Patients with Prader-Willi syndrome should be evaluated for signs of upper airway obstruction and sleep apnea before initiation of treatment with somatropin. If during treatment with somatropin, patients show signs of upper airway obstruction (including onset of or increased snoring) and/or new onset sleep apnea, treatment should be interrupted. All patients with Prader-Willi syndrome treated with somatropin should also have effective weight control and be monitored for signs of respiratory infection, which should be diagnosed as early as possible and treated aggressively [see Contraindications (4)].

5.3 Neoplasms

In childhood cancer survivors who were treated with radiation to the brain/head for their first neoplasm and who developed subsequent GHD and were treated with somatropin, an increased risk of a second neoplasm has been reported. Intracranial tumors, in particular meningiomas, were the most common of these second neoplasms. In adults, it is unknown whether there is any relationship between somatropin replacement therapy and CNS tumor recurrence [see Contraindications (4)].

Monitor all patients with a history of GHD secondary to an intracranial neoplasm routinely while on somatropin therapy for progression or recurrence of the tumor.

Because children with certain rare genetic causes of short stature have an increased risk of developing malignancies, practitioners should thoroughly consider the risks and benefits of starting somatropin in these patients. If treatment with somatropin is initiated, these patients should be carefully monitored for development of neoplasms.

Monitor patients on somatropin therapy carefully for increased growth, or potential malignant changes, of preexisting nevi.

5.4 Impaired Glucose Tolerance and Diabetes Mellitus

Treatment with somatropin may decrease insulin sensitivity, particularly at higher doses in susceptible patients. As a result, previously undiagnosed impaired glucose tolerance and overt diabetes mellitus may be unmasked during somatropin treatment. New-onset Type 2 diabetes mellitus has been reported. Therefore, glucose levels should be monitored periodically in all patients treated with somatropin, especially in those with risk factors for diabetes mellitus, such as obesity, Turner syndrome, or a family history of diabetes mellitus. Patients with preexisting type 1 or type 2 diabetes mellitus or impaired glucose tolerance should be monitored closely during somatropin therapy. The doses of antihyperglycemic drugs (i.e., insulin or oral/injectable agents) may require adjustment when somatropin therapy is instituted in these patients.

5.5 Intracranial Hypertension

Intracranial hypertension (IH) with papilledema, visual changes, headache, nausea and/or vomiting has been reported in a small number of patients treated with somatropins. Symptoms usually occurred within the first eight (8) weeks after the initiation of somatropin therapy. In all reported cases, IH-associated signs and symptoms rapidly resolved after cessation of therapy or a reduction of the somatropin dose. Fundoscopic examination should be performed routinely before initiating treatment with somatropin to exclude preexisting papilledema, and periodically during the course of somatropin therapy. If papilledema is observed by fundoscopy during somatropin treatment, treatment should be stopped. If somatropin-induced IH is diagnosed, treatment with somatropin can be restarted at a lower dose after IH-associated signs and symptoms have resolved. Patients with Turner syndrome and Prader-Willi syndrome may be at increased risk for the development of IH.

5.6 Severe Hypersensitivity

Serious systemic hypersensitivity reactions including anaphylactic reactions and angioedema have been reported with postmarketing use of somatropins. Patients and caregivers should be informed that such reactions are possible and that prompt medical attention should be sought if an allergic reaction occurs [see Contraindications (4)].

5.7 Fluid Retention

Fluid retention during somatropin replacement therapy in adults may occur. Clinical manifestations of fluid retention (e.g., edema, arthralgia, myalgia, nerve compression syndromes including carpal tunnel syndrome/paresthesia) are usually transient and dose dependent.

5.8 Hypoadrenalism

Patients receiving somatropin therapy who have or are at risk for pituitary hormone deficiency(s) may be at risk for reduced serum cortisol levels and/or unmasking of central (secondary) hypoadrenalism. In addition, patients treated with glucocorticoid replacement for previously diagnosed hypoadrenalism may require an increase in their maintenance or stress doses following initiation of somatropin treatment [see Drug Interactions (7.1)].

5.9 Hypothyroidism

Undiagnosed/untreated hypothyroidism may prevent an optimal response to somatropin, in particular, the growth response in children. Patients with Turner syndrome have an inherently increased risk of developing autoimmune thyroid disease and primary hypothyroidism. In patients with growth hormone deficiency, central (secondary) hypothyroidism may first become evident or worsen during somatropin treatment. Therefore, patients treated with somatropin should have periodic thyroid function tests and thyroid hormone replacement therapy should be initiated or appropriately adjusted when indicated.

5.10 Slipped Capital Femoral Epiphyses in Pediatric Patients

Slipped capital femoral epiphyses may occur more frequently in patients with endocrine disorders (including GHD and Turner syndrome) or in patients undergoing rapid growth. Slipped capital femoral epiphysis may lead to osteonecrosis. Cases of slipped capital femoral epiphysis with or without osteonecrosis have been reported in pediatric patients with short stature receiving somatropin, including GENOTROPIN. Any pediatric patient with the onset of a limp or complaints of hip or knee pain during GENOTROPIN therapy should be evaluated for slipped capital femoral epiphysis and osteonecrosis and managed accordingly.

5.11 Progression of Preexisting Scoliosis in Pediatric Patients

Progression of scoliosis can occur in patients who experience rapid growth. Because somatropin increases growth rate, patients with a history of scoliosis who are treated with somatropin should be monitored for progression of scoliosis. However, somatropin has not been shown to increase the occurrence of scoliosis. Skeletal abnormalities including scoliosis are commonly seen in untreated Turner syndrome patients. Scoliosis is also commonly seen in untreated patients with Prader-Willi syndrome. Physicians should be alert to these abnormalities, which may manifest during somatropin therapy.

5.12 Otitis Media and Cardiovascular Disorders in Turner Syndrome

Patients with Turner syndrome should be evaluated carefully for otitis media and other ear disorders since these patients have an increased risk of ear and hearing disorders. Somatropin treatment may increase the occurrence of otitis media in patients with Turner syndrome. In addition, patients with Turner syndrome should be monitored closely for cardiovascular disorders (e.g., stroke, aortic aneurysm/dissection, hypertension) as these patients are also at risk for these conditions.

5.13 Lipoatrophy

When somatropin is administered subcutaneously at the same site over a long period of time, tissue atrophy may result. This can be avoided by rotating the injection site [see Dosage and Administration (2.3)].

5.14 Laboratory Tests

Serum levels of inorganic phosphorus, alkaline phosphatase, parathyroid hormone (PTH) and IGF-I may increase during somatropin therapy.

5.15 Pancreatitis

Cases of pancreatitis have been reported rarely in children and adults receiving somatropin treatment, with some evidence supporting a greater risk in children compared with adults. Published literature indicates that girls who have Turner syndrome may be at greater risk than other somatropin-treated children. Pancreatitis should be considered in any somatropin–treated patient, especially a child, who develops persistent severe abdominal pain.

6 ADVERSE REACTIONS

The following important adverse reactions are also described elsewhere in the labeling:

- Increased mortality in patients with acute critical illness [see Warnings and Precautions (5.1)]
- Fatalities in children with Prader-Willi syndrome [see Warnings and Precautions (5.2)]
- Neoplasms [see Warnings and Precautions (5.3)]
- Glucose intolerance and diabetes mellitus [see Warnings and Precautions (5.4)]
- Intracranial hypertension [see Warnings and Precautions (5.5)]
- Severe hypersensitivity [see Warnings and Precautions (5.6)]
- Fluid retention [see Warnings and Precautions (5.7)]
- Hypoadrenalism [see Warnings and Precautions (5.8)]
- Hypothyroidism [see Warnings and Precautions (5.9)]
- Slipped capital femoral epiphysis in pediatric patients [see Warnings and Precautions (5.10)]
- Progression of preexisting scoliosis in pediatric patients [see Warnings and Precautions (5.11)]
- Otitis media and cardiovascular disorders in patients with Turner syndrome [see Warnings and Precautions (5.12)]
- Lipoatrophy [see Warnings and Precautions (5.13)]
- Pancreatitis [see Warnings and Precautions (5.15)]

6.1 Clinical Trials Experience

Because clinical trials are conducted under varying conditions, adverse reaction rates observed during the clinical trials performed with one somatropin formulation cannot always be directly compared to the rates observed during the clinical trials performed with a second somatropin formulation, and may not reflect the adverse reaction rates observed in practice.

Clinical Trials in children with GHD

In clinical studies with GENOTROPIN in pediatric GHD patients, the following events were reported infrequently: injection site reactions, including pain or burning associated with the injection, fibrosis, nodules, rash, inflammation, pigmentation, or bleeding; lipoatrophy; headache; hematuria; hypothyroidism; and mild hyperglycemia.

Clinical Trials in PWS

In two clinical studies with GENOTROPIN in pediatric patients with Prader-Willi syndrome, the following drug-related events were reported: edema, aggressiveness, arthralgia, benign intracranial hypertension, hair loss, headache, and myalgia.

Clinical Trials in children with SGA

In clinical studies of 273 pediatric patients born small for gestational age treated with GENOTROPIN, the following clinically significant events were reported: mild transient hyperglycemia, one patient with benign intracranial hypertension, two patients with central precocious puberty, two patients with jaw prominence, and several patients with aggravation of preexisting scoliosis, injection site reactions, and self-limited progression of pigmented nevi. Anti-hGH antibodies were not detected in any of the patients treated with GENOTROPIN.

Clinical Trials in children with Turner Syndrome

In two clinical studies with GENOTROPIN in pediatric patients with Turner syndrome, the most frequently reported adverse events were respiratory illnesses (influenza, tonsillitis, otitis, sinusitis), joint pain, and urinary tract infection. The only treatment-related adverse event that occurred in more than 1 patient was joint pain.

Clinical Trials in children with Idiopathic Short Stature

In two open-label clinical studies with GENOTROPIN in pediatric patients with ISS, the most commonly encountered adverse events include upper respiratory tract infections, influenza, tonsillitis, nasopharyngitis, gastroenteritis, headaches, increased appetite, pyrexia, fracture, altered mood, and arthralgia. In one of the two studies, during GENOTROPIN treatment, the mean IGF-1 standard deviation (SD) scores were maintained in the normal range. IGF-1 SD scores above +2 SD were observed as follows: 1 subject (3%), 10 subjects (30%) and 16 subjects (38%) in the untreated control, 0. 23 and the 0.47 mg/kg/week groups, respectively, had at least one measurement; while 0 subjects (0%), 2 subjects (7%) and 6 subjects (14%) had two or more consecutive IGF-1 measurements above +2 SD.

Clinical Trials in adults with GHD

In clinical trials with GENOTROPIN in 1,145 GHD adults, the majority of the adverse events consisted of mild to moderate symptoms of fluid retention, including peripheral swelling, arthralgia, pain and stiffness of the extremities, peripheral edema, myalgia, paresthesia, and hypoesthesia. These events were reported early during therapy and tended to be transient and/or responsive to dosage reduction.

Table 1 displays the adverse events reported by 5% or more of adult GHD patients in clinical trials after various durations of treatment with GENOTROPIN. Also presented are the corresponding incidence rates of these adverse events in placebo patients during the 6-month double-blind portion of the clinical trials.

Table 1. Adverse Events Reported by ≥ 5% of 1,145 Adult GHD Patients During Clinical Trials of GENOTROPIN and Placebo, Grouped by Duration of Treatment
 | Double Blind Phase |  | Open Label Phase GENOTROPIN
Adverse Event | Placebo 0–6 mo. n = 572 % Patients | GENOTROPIN 0–6 mo. n = 573 % Patients | 6–12 mo. n = 504 % Patients | 12–18 mo. n = 63 % Patients | 18–24 mo. n = 60 % Patients
Swelling, peripheral | 5.1 | 17.5 [Increased significantly when compared to placebo, P≤.025: Fisher´s Exact Test (one-sided)] | 5.6 | 0 | 1.7
Arthralgia | 4.2 | 17.3 | 6.9 | 6.3 | 3.3
Upper respiratory infection | 14.5 | 15.5 | 13.1 | 15.9 | 13.3
Pain, extremities | 5.9 | 14.7 | 6.7 | 1.6 | 3.3
Edema, peripheral | 2.6 | 10.8 | 3.0 | 0 | 0
Paresthesia | 1.9 | 9.6 | 2.2 | 3.2 | 0
Headache | 7.7 | 9.9 | 6.2 | 0 | 0
Stiffness of extremities | 1.6 | 7.9 | 2.4 | 1.6 | 0
Fatigue | 3.8 | 5.8 | 4.6 | 6.3 | 1.7
Myalgia | 1.6 | 4.9 | 2.0 | 4.8 | 6.7
Back pain | 4.4 | 2.8 | 3.4 | 4.8 | 5.0
n = number of patients receiving treatment during the indicated period.
%= percentage of patients who reported the event during the indicated period.

Post-Trial Extension Studies in Adults

In expanded post-trial extension studies, diabetes mellitus developed in 12 of 3,031 patients (0.4%) during treatment with GENOTROPIN. All 12 patients had predisposing factors, e.g., elevated glycated hemoglobin levels and/or marked obesity, prior to receiving GENOTROPIN. Of the 3,031 patients receiving GENOTROPIN, 61 (2%) developed symptoms of carpal tunnel syndrome, which lessened after dosage reduction or treatment interruption (52) or surgery (9). Other adverse events that have been reported include generalized edema and hypoesthesia.

Periplasmic Escherichia coli Peptides

Preparations of GENOTROPIN contain a small amount of periplasmic Escherichia coli peptides (PECP). Anti-PECP antibodies are found in a small number of patients treated with GENOTROPIN, but these appear to be of no clinical significance.

6.2 Postmarketing Experience

The following adverse reactions have been identified during post-approval use of somatropin or GENOTROPIN. Because these adverse events are reported voluntarily from a population of uncertain size, it is not always possible to reliably estimate their frequency or establish a causal relationship to drug exposure.

Serious systemic hypersensitivity reactions including anaphylactic reactions and angioedema have been reported with postmarketing use of somatropins [see Warnings and Precautions (5.6)].

Leukemia has been reported in a small number of GHD children treated with somatropin, somatrem (methionylated rhGH) and GH of pituitary origin. It is uncertain whether these cases of leukemia are related to GH therapy, the pathology of GHD itself, or other associated treatments such as radiation therapy. On the basis of current evidence, experts have not been able to conclude that GH therapy per se was responsible for these cases of leukemia. The risk for children with GHD, if any, remains to be established [see Contraindications (4) and Warnings and Precautions (5.3)].

The following serious adverse reactions have been observed with use of somatropin (including events observed in patients who received brands of somatropin other than GENOTROPIN): acute critical illness [see Warnings and Precautions (5.1)], sudden death [see Warnings and Precautions (5.2)], intracranial tumors [see Warnings and Precautions (5.3)], central hypothyroidism [see Warnings and Precautions (5.9)], cardiovascular disorders, and pancreatitis [see Warnings and Precautions (5.15)].

Slipped capital femoral epiphysis and osteonecrosis/avascular necrosis (including Legg-Calvé-Perthes disease) have been reported in children treated with growth hormone [see Warnings and Precautions (5.10)]. Cases have been reported with GENOTROPIN.

The following additional adverse reactions have been observed during the appropriate use of somatropin: headaches (children and adults), gynecomastia (children), and significant diabetic retinopathy.

New-onset type 2 diabetes mellitus has been reported.

7 DRUG INTERACTIONS

7.1 11 β-Hydroxysteroid Dehydrogenase Type 1

The microsomal enzyme 11β-hydroxysteroid dehydrogenase type 1 (11βHSD-1) is required for conversion of cortisone to its active metabolite, cortisol, in hepatic and adipose tissue. GH and somatropin inhibit 11βHSD-1. Consequently, individuals with untreated GH deficiency have relative increases in 11βHSD-1 and serum cortisol. Introduction of somatropin treatment may result in inhibition of 11βHSD-1 and reduced serum cortisol concentrations. As a consequence, previously undiagnosed central (secondary) hypoadrenalism may be unmasked and glucocorticoid replacement may be required in patients treated with somatropin. In addition, patients treated with glucocorticoid replacement for previously diagnosed hypoadrenalism may require an increase in their maintenance or stress doses following initiation of somatropin treatment; this may be especially true for patients treated with cortisone acetate and prednisone since conversion of these drugs to their biologically active metabolites is dependent on the activity of 11βHSD-1 [see Warnings and Precautions (5.8)].

7.2 Pharmacologic Glucocorticoid Therapy and Supraphysiologic Glucocorticoid Treatment

Pharmacologic glucocorticoid therapy and supraphysiologic glucocorticoid treatment may attenuate the growth‑promoting effects of somatropin in children. Therefore, glucocorticoid replacement dosing should be carefully adjusted in children receiving concomitant somatropin and glucocorticoid treatments to avoid both hypoadrenalism and an inhibitory effect on growth.

7.3 Cytochrome P450-Metabolized Drugs

Limited published data indicate that somatropin treatment increases cytochrome P450 (CYP450)-mediated antipyrine clearance in man. These data suggest that somatropin administration may alter the clearance of compounds known to be metabolized by CYP450 liver enzymes (e.g., corticosteroids, sex steroids, anticonvulsants, cyclosporine). Careful monitoring is advisable when somatropin is administered in combination with other drugs known to be metabolized by CYP450 liver enzymes. However, formal drug interaction studies have not been conducted.

7.4 Oral Estrogen

In patients on oral estrogen replacement, a larger dose of somatropin may be required to achieve the defined treatment goal [see Dosage and Administration (2.2)].

7.5 Insulin and/or Oral/Injectable Hypoglycemic Agents

In patients with diabetes mellitus requiring drug therapy, the dose of insulin and/or oral/injectable agent may require adjustment when somatropin therapy is initiated [see Warnings and Precautions (5.4)].

8 USE IN SPECIFIC POPULATIONS

8.1 Pregnancy

Risk Summary

Limited available data with somatropin use in pregnant women are insufficient to determine a drug-associated risk of adverse developmental outcomes. In animal studies (rats and rabbits), there was no evidence of embryo‑fetal or neonatal harm following somatropin administration during organogenesis at doses approximately 24 times and 19 times the recommended human therapeutic levels, respectively, based on body surface area (see Data).

The estimated background risk of birth defects and miscarriage for the indicated population is unknown. In the U.S. general population, the estimated background risk of major birth defects and miscarriage in clinically recognized pregnancies is 2-4% and 15-20%, respectively.

Data

Animal Data

Animal reproduction studies with somatropin during the period of organogenesis at doses of 0.3, 1, and 3.3 mg/kg/day administered subcutaneously (SC) in pregnant rats and 0.08, 0.3, and 1.3 mg/kg/day administered intramuscularly in pregnant rabbits were not teratogenic (highest doses approximately 24 times and 19 times the recommended human therapeutic levels, respectively, based on body surface area).

In perinatal and postnatal studies in rats, somatropin doses of 0.3, 1, and 3.3 mg/kg/day produced growth‑promoting effects in the dams but not in the fetuses. Young rats at the highest dose showed increased weight gain during suckling but the effect was not apparent by 10 weeks of age. No adverse effects were observed on gestation, morphogenesis, parturition, lactation, postnatal development, or reproductive capacity of the offspring due to somatropin.

8.2 Lactation

Risk Summary

There is no information regarding the presence of somatropin in human milk. Limited published data indicate that exogenous somatropin does not increase normal breastmilk concentrations of growth hormone. No adverse effects related to somatropin in the breastfeed infant have been reported. The developmental and health benefits of breastfeeding should be considered along with the mother’s clinical need for GENOTROPIN and any potential adverse effects on the breastfed infant from GENOTROPIN or from the underlying maternal condition.

8.4 Pediatric Use

Safety and effectiveness of GENOTROPIN in pediatric patients have been established in growth failure due to Prader-Willi syndrome (PWS), growth failure in children born small for gestational age (SGA) with no catch-up growth by age 2 years, growth failure associated with Turner syndrome, idiopathic short stature (ISS) and growth failure due to inadequate secretion of endogenous growth hormone.

Growth Failure Due to Prader-Willi Syndrome (PWS)

Safety and effectiveness of GENOTROPIN have been established in pediatric patients with growth failure due to Prader-Willi syndrome based on data from two randomized, open-label, controlled clinical trials with GENOTROPIN in 43 pediatric patients. There have been reports of sudden death after initiating therapy with somatropin in pediatric patients with Prader-Willi syndrome who had one or more of the following risk factors: severe obesity, history of upper airway obstruction or sleep apnea, or unidentified respiratory infection. Male patients with one or more of these factors may be at greater risk than females. Patients with Prader-Willi syndrome should be evaluated for signs of upper airway obstruction and sleep apnea before initiation of treatment with somatropin [see Contraindications (4), Warnings and Precautions (5.2), Clinical Studies (14.2)].

Short Stature in Pediatric Patients Born Small for Gestational Age (SGA) with No Catch-up Growth by Age 2

Safety and effectiveness of GENOTROPIN have been established in pediatric patients with short stature born SGA with no catch-up growth based on data from 4 randomized, open-label, controlled clinical trials with GENOTROPIN in 209 pediatric patients [see Clinical Studies (14.3)].

Short Stature associated with Turner Syndrome

Safety and effectiveness of GENOTROPIN have been established in pediatric patients with short stature associated with Turner syndrome based on data from two randomized, open-label, clinical trials with GENOTROPIN in 38 pediatric patients [see Clinical Studies (14.4)].

Idiopathic Short Stature (ISS)

Safety and effectiveness of GENOTROPIN have been established in pediatric patients with ISS based on data from one randomized, open-label, clinical trial with GENOTROPIN in 102 pediatric patients [see Clinical Studies (14.5)].

8.5 Geriatric Use

The safety and effectiveness of GENOTROPIN in patients aged 65 and over have not been evaluated in clinical studies. Elderly patients may be more sensitive to the action of GENOTROPIN, and therefore may be more prone to develop adverse reactions. A lower starting dose and smaller dose increments should be considered for older patients [see Dosage and Administration (2.2)].

10 OVERDOSAGE

Short-Term

Short-term overdosage could lead initially to hypoglycemia and subsequently to hyperglycemia. Furthermore, overdose with somatropin is likely to cause fluid retention.

Long-Term

Long-term overdosage could result in signs and symptoms of gigantism and/or acromegaly consistent with the known effects of excess growth hormone [see Dosage and Administration (2)].

11 DESCRIPTION

Somatropin is a human growth hormone produced by recombinant DNA technology in Escherichia coli. The protein is comprised of 191 amino acid residues and has a molecular weight of 22,124 daltons. The amino acid sequence is identical to that of human growth hormone of pituitary origin.

GENOTROPIN (somatropin) for injection is a sterile, white, lyophilized powder in a single-patient-use or single-dose, two-chamber cartridge intended for subcutaneous injection after reconstitution. The front chamber contains somatropin and the rear chamber contains diluent.

GENOTROPIN 5 mg is a single-patient-use, two-chamber cartridge. GENOTROPIN 5 mg is designed for use with a reusable device (GENOTROPIN PEN 5) for product reconstitution and drug delivery. After reconstitution, each mL contains 5 mg of somatropin, dibasic sodium phosphate (0.27 mg), glycine (2 mg), mannitol (41 mg), metacresol (3 mg) (as a preservative), monobasic sodium phosphate (0.28 mg) and water for injection. The reconstituted concentration is 5 mg/mL with a deliverable volume of 1 mL.

GENOTROPIN 12 mg is a single‑patient‑use, two-chamber cartridge. GENOTROPIN 12 mg is designed for use with a reusable device (GENOTROPIN PEN 12) for product reconstitution and drug delivery. After reconstitution, each mL contains 12 mg of somatropin, dibasic sodium phosphate (0.4 mg), glycine (2 mg), mannitol (40 mg), metacresol (3 mg) (as a preservative), monobasic sodium phosphate (0.41 mg) and water for injection. The reconstituted concentration is 12 mg/mL with a deliverable volume of 1 mL.

GENOTROPIN MINIQUICK is a single-dose Growth Hormone Delivery Device containing a two-chamber cartridge supplied in the following strengths: 0.2 mg, 0.4 mg, 0.6 mg, 0.8 mg, 1 mg, 1.2 mg, 1.4 mg, 1.6 mg, 1.8 mg, or 2 mg. After reconstitution, each 0.25 mL contains 0.2 mg, 0.4 mg, 0.6 mg, 0.8 mg, 1 mg, 1.2 mg, 1.4 mg, 1.6 mg, 1.8 mg, or 2 mg of somatropin, dibasic sodium phosphate (0.03 mg), glycine (0.21 mg), mannitol (12.5 mg), monobasic sodium phosphate (0.05 mg) and water for injection. Each cartridge provides a deliverable volume of 0.25 mL.

The reconstituted recombinant somatropin solution has an osmolality of approximately 300 mOsm/kg, and a pH of approximately 6.7.

12 CLINICAL PHARMACOLOGY

12.1 Mechanism of Action

In vitro, preclinical, and clinical tests have demonstrated that GENOTROPIN lyophilized powder is therapeutically equivalent to human growth hormone of pituitary origin and achieves similar pharmacokinetic profiles in normal adults. In pediatric patients who have growth hormone deficiency (GHD), have Prader-Willi syndrome (PWS), were born small for gestational age (SGA), have Turner syndrome (TS), or have Idiopathic short stature (ISS), treatment with GENOTROPIN stimulates linear growth. In patients with GHD or PWS, treatment with GENOTROPIN also normalizes concentrations of IGF-I (Insulin-like Growth Factor-I/Somatomedin C). In adults with GHD, treatment with GENOTROPIN results in reduced fat mass, increased lean body mass, metabolic alterations that include beneficial changes in lipid metabolism, and normalization of IGF-I concentrations.

In addition, the following actions have been demonstrated for GENOTROPIN and/or somatropin.

12.2 Pharmacodynamics

Tissue Growth

A. Skeletal Growth: GENOTROPIN stimulates skeletal growth in pediatric patients with GHD, PWS, SGA, TS, or ISS. The measurable increase in body length after administration of GENOTROPIN results from an effect on the epiphyseal plates of long bones. Concentrations of IGF-I, which may play a role in skeletal growth, are generally low in the serum of pediatric patients with GHD, PWS, or SGA, but tend to increase during treatment with GENOTROPIN. Elevations in mean serum alkaline phosphatase concentration are also seen.
B. Cell Growth: It has been shown that there are fewer skeletal muscle cells in short-statured pediatric patients who lack endogenous growth hormone as compared with the normal pediatric population. Treatment with somatropin results in an increase in both the number and size of muscle cells.

Protein Metabolism

Linear growth is facilitated in part by increased cellular protein synthesis. Nitrogen retention, as demonstrated by decreased urinary nitrogen excretion and serum urea nitrogen, follows the initiation of therapy with GENOTROPIN.

Carbohydrate Metabolism

Pediatric patients with hypopituitarism sometimes experience fasting hypoglycemia that is improved by treatment with GENOTROPIN. Large doses of growth hormone may impair glucose tolerance.

Lipid Metabolism

In GHD patients, administration of somatropin has resulted in lipid mobilization, reduction in body fat stores, and increased plasma fatty acids.

Mineral Metabolism

Somatropin induces retention of sodium, potassium, and phosphorus. Serum concentrations of inorganic phosphate are increased in patients with GHD after therapy with GENOTROPIN. Serum calcium is not significantly altered by GENOTROPIN. Growth hormone could increase calciuria.

Body Composition

Adult GHD patients treated with GENOTROPIN at the recommended adult dose [see Dosage and Administration (2)] demonstrate a decrease in fat mass and an increase in lean body mass. When these alterations are coupled with the increase in total body water, the overall effect of GENOTROPIN is to modify body composition, an effect that is maintained with continued treatment.

12.3 Pharmacokinetics

Absorption

Following a 0.03 mg/kg subcutaneous (SC) injection in the thigh of 1.3 mg/mL GENOTROPIN to adult GHD patients, approximately 80% of the dose was systemically available as compared with that available following intravenous dosing. Results were comparable in both male and female patients. Similar bioavailability has been observed in healthy adult male subjects.

In healthy adult males, following an SC injection in the thigh of 0.03 mg/kg, the extent of absorption (AUC) of a concentration of 5.3 mg/mL GENOTROPIN was 35% greater than that for 1.3 mg/mL GENOTROPIN. The mean (± standard deviation) peak (Cmax) serum levels were 23.0 (± 9.4) ng/mL and 17.4 (± 9.2) ng/mL, respectively.

In a similar study involving pediatric GHD patients, 5.3 mg/mL GENOTROPIN yielded a mean AUC that was 17% greater than that for 1.3 mg/mL GENOTROPIN. The mean Cmax levels were 21.0 ng/mL and 16.3 ng/mL, respectively.

Adult GHD patients received two single SC doses of 0.03 mg/kg of GENOTROPIN at a concentration of 1.3 mg/mL, with a one- to four-week washout period between injections. Mean Cmax levels were 12.4 ng/mL (first injection) and 12.2 ng/mL (second injection), achieved at approximately six hours after dosing.

There are no data on the bioequivalence between the 12 mg/mL formulation and either the 1.3 mg/mL or the 5.3 mg/mL formulations.

Distribution

The mean volume of distribution of GENOTROPIN following administration to GHD adults was estimated to be 1.3 (± 0.8) L/kg.

Metabolism

The metabolic fate of GENOTROPIN involves classical protein catabolism in both the liver and kidneys. In renal cells, at least a portion of the breakdown products are returned to the systemic circulation. The mean terminal half-life of intravenous GENOTROPIN in normal adults is 0.4 hours, whereas subcutaneously administered GENOTROPIN has a half-life of 3.0 hours in GHD adults. The observed difference is due to slow absorption from the subcutaneous injection site.

Excretion

The mean clearance of subcutaneously administered GENOTROPIN in 16 GHD adult patients was 0.3 (± 0.11) L/hrs/kg.

Special Populations

Pediatric: The pharmacokinetics of GENOTROPIN are similar in GHD pediatric and adult patients.

Gender: No gender studies have been performed in pediatric patients; however, in GHD adults, the absolute bioavailability of GENOTROPIN was similar in males and females.

Race: No studies have been conducted with GENOTROPIN to assess pharmacokinetic differences among races.

Renal or hepatic insufficiency: No studies have been conducted with GENOTROPIN in these patient populations.

Table 2. Mean SC Pharmacokinetic Parameters in Adult GHD Patients
 | Bioavailability (%) (N=15) | Tmax (hours) (N=16) | CL/F (L/hr × kg) (N=16) | Vss/F (L/kg) (N=16) | T1/2 (hours) (N=16)
Mean | 80.5 | 5.9 | 0.3 | 1.3 | 3.0
(± SD) | [The absolute bioavailability was estimated under the assumption that the log-transformed data follow a normal distribution. The mean and standard deviation of the log-transformed data were mean = 0.22 (± 0.241).] | (± 1.65) | (± 0.11) | (± 0.80) | (± 1.44)
95% CI | 70.5 – 92.1 | 5.0 – 6.7 | 0.2 – 0.4 | 0.9 – 1.8 | 2.2 – 3.7
Tmax = time of maximum plasma concentration
CL/F = plasma clearance
Vss/F = volume of distribution
T 1/2 = terminal half-life
SD = standard deviation
CI = confidence interval

12.6 Immunogenicity

The observed incidence of anti-drug antibodies is highly dependent on the sensitivity and specificity of the assay. Differences in assay methods preclude meaningful comparisons of the incidence of anti-drug antibodies in the studies described below with the incidence of anti-drug antibodies in other studies, including those of GENOTROPIN or other somatropins.

In the case of growth hormone, antibodies with binding capacities lower than 2 mg/mL have not been associated with growth attenuation. In a very small number of patients treated with somatropin, when binding capacity was greater than 2 mg/mL, interference with the growth response was observed.

In 419 pediatric patients evaluated in clinical studies with GENOTROPIN lyophilized powder, 244 had been treated previously with GENOTROPIN or other growth hormone preparations and 175 had received no previous growth hormone therapy. Antibodies to growth hormone (anti-hGH antibodies) were present in six previously treated patients at baseline. Three of the six became negative for anti-hGH antibodies during 6 to 12 months of treatment with GENOTROPIN. Of the remaining 413 patients, eight (1.9%) developed detectable anti-hGH antibodies during treatment with GENOTROPIN; none had an antibody binding capacity >2 mg/L. There was no evidence that the growth response to GENOTROPIN was affected in these antibody-positive patients.

13 NONCLINICAL TOXICOLOGY

13.1 Carcinogenesis, Mutagenesis, Impairment of Fertility

Carcinogenicity studies have not been conducted with GENOTROPIN. No potential mutagenicity of GENOTROPIN was revealed in a battery of tests including induction of gene mutations in bacteria (the Ames test), gene mutations in mammalian cells grown in vitro (mouse L5178Y cells), and chromosomal damage in intact animals (bone marrow cells in rats).

In a fertility study in male and female rats receiving SC doses during gametogenesis (2 weeks prior to mating for females and 9 weeks prior to mating for males) and continuing up to 7 days of pregnancy, 3.3 mg/kg/day (approximately 24 times human dose by body surface area) produced anestrus or extended estrus cycles in females and fewer and less motile sperm in males. Lower copulation and pregnancy rates were also observed at 3.3 mg/kg/day. At 1 mg/kg/day (approximately 7 times human dose by body surface area), rats showed slightly extended estrus cycles, whereas at 0.3 mg/kg/day no effects were noted (approximately 2 times human dose by body surface).

14 CLINICAL STUDIES

14.1 Adult Growth Hormone Deficiency (GHD)

GENOTROPIN lyophilized powder was compared with placebo in six randomized clinical trials involving a total of 172 adult GHD patients. These trials included a 6-month double-blind treatment period, during which 85 patients received GENOTROPIN and 87 patients received placebo, followed by an open-label treatment period in which participating patients received GENOTROPIN for up to a total of 24 months. GENOTROPIN was administered as a daily SC injection at a dose of 0.04 mg/kg/week for the first month of treatment and 0.08 mg/kg/week for subsequent months.

Beneficial changes in body composition were observed at the end of the 6-month treatment period for the patients receiving GENOTROPIN as compared with the placebo patients. Lean body mass, total body water, and lean/fat ratio increased while total body fat mass and waist circumference decreased. These effects on body composition were maintained when treatment was continued beyond 6 months. Bone mineral density declined after 6 months of treatment but returned to baseline values after 12 months of treatment.

14.2 Prader-Willi Syndrome (PWS)

The safety and efficacy of GENOTROPIN in the treatment of pediatric patients with Prader-Willi syndrome (PWS) were evaluated in two randomized, open-label, controlled clinical trials. Patients received either GENOTROPIN or no treatment for the first year of the studies, while all patients received GENOTROPIN during the second year. GENOTROPIN was administered as a daily SC injection, and the dose was calculated for each patient every 3 months. In Study 1, the treatment group received GENOTROPIN at a dose of 0.24 mg/kg/week during the entire study. During the second year, the control group received GENOTROPIN at a dose of 0.48 mg/kg/week. In Study 2, the treatment group received GENOTROPIN at a dose of 0.36 mg/kg/week during the entire study. During the second year, the control group received GENOTROPIN at a dose of 0.36 mg/kg/week.

Patients who received GENOTROPIN showed significant increases in linear growth during the first year of study, compared with patients who received no treatment (see Table 3). Linear growth continued to increase in the second year, when both groups received treatment with GENOTROPIN.

Table 3. Efficacy of GENOTROPIN in Pediatric Patients with Prader-Willi Syndrome (Mean ± SD)
 | Study 1 |  | Study 2
 | GENOTROPIN | Untreated Control n=12 | GENOTROPIN | Untreated Control n=9
 | (0.24 mg/kg/week) n=15 | Untreated Control n=12 | (0.36 mg/kg/week) n=7 | Untreated Control n=9
Linear growth (cm) Baseline height | 112.7 ± 14.9 | 109.5 ± 12.0 | 120.3 ± 17.5 | 120.5 ± 11.2
Growth from months 0 to 12 | 11.6 [p ≤ 0.001] ± 2.3 | 5.0 ± 1.2 | 10.7 ± 2.3 | 4.3 ± 1.5
Height Standard Deviation Score (SDS) for age Baseline SDS | -1.6 ± 1.3 | -1.8 ± 1.5 | -2.6 ± 1.7 | -2.1 ± 1.4
SDS at 12 months | -0.5 [p ≤ 0.002 (when comparing SDS change at 12 months)] ± 1.3 | -1.9 ± 1.4 | -1.4 ± 1.5 | -2.2 ± 1.4

Changes in body composition were also observed in the patients receiving GENOTROPIN (see Table 4). These changes included a decrease in the amount of fat mass, and increases in the amount of lean body mass and the ratio of lean-to-fat tissue, while changes in body weight were similar to those seen in patients who received no treatment. Treatment with GENOTROPIN did not accelerate bone age, compared with patients who received no treatment.

Table 4. Effect of GENOTROPIN on Body Composition in Pediatric Patients with Prader-Willi Syndrome (Mean ± SD)
 | GENOTROPIN | Untreated Control n=10
 | n=14 | Untreated Control n=10
Fat mass (kg)
Baseline | 12.3 ± 6.8 | 9.4 ± 4.9
Change from months 0 to 12 | -0.9 [p < 0.005] ± 2.2 | 2.3 ± 2.4
Lean body mass (kg)
Baseline | 15.6 ± 5.7 | 14.3 ± 4.0
Change from months 0 to 12 | 4.7 ± 1.9 | 0.7 ± 2.4
Lean body mass/Fat mass
Baseline | 1.4 ± 0.4 | 1.8 ± 0.8
Change from months 0 to 12 | 1.0 ± 1.4 | -0.1 ± 0.6
Body weight (kg) [n=15 for the group receiving GENOTROPIN; n=12 for the Control group]
Baseline | 27.2 ± 12.0 | 23.2 ± 7.0
Change from months 0 to 12 | 3.7 [n.s.] ± 2.0 | 3.5 ± 1.9

14.3 Small for Gestational Age

Pediatric Patients Born Small for Gestational Age (SGA) Who Fail to Manifest Catch-up Growth by Age 2

The safety and efficacy of GENOTROPIN in the treatment of pediatric patients born small for gestational age (SGA) were evaluated in 4 randomized, open-label, controlled clinical trials. Patients (age range of 2 to 8 years) were observed for 12 months before being randomized to receive either GENOTROPIN (two doses per study, most often 0.24 and 0.48 mg/kg/week) as a daily SC injection or no treatment for the first 24 months of the studies. After 24 months in the studies, all patients received GENOTROPIN.

Patients who received any dose of GENOTROPIN showed significant increases in growth during the first 24 months of study, compared with patients who received no treatment (see Table 5). Children receiving 0.48 mg/kg/week demonstrated a significant improvement in height standard deviation score (SDS) compared with children treated with 0.24 mg/kg/week. Both of these doses resulted in a slower but constant increase in growth between months 24 to 72 (data not shown).

Table 5. Efficacy of GENOTROPIN in Pediatric Patients Born Small for Gestational Age (Mean ± SD)
 | GENOTROPIN | GENOTROPIN | Untreated Control n=40
 | (0.24 mg/kg/week) n=76 | (0.48 mg/kg/week) n=93 | Untreated Control n=40
Height Standard Deviation Score (SDS)
Baseline SDS | -3.2 ± 0.8 | -3.4 ± 1.0 | -3.1 ± 0.9
SDS at 24 months | -2.0 ± 0.8 | -1.7 ± 1.0 | -2.9 ± 0.9
Change in SDS from baseline to month 24 | 1.2 [p = 0.0001 vs Untreated Control group] ± 0.5 | 1.7 [p = 0.0001 vs group treated with GENOTROPIN 0.24 mg/kg/week] ± 0.6 | 0.1 ± 0.3

14.4 Turner Syndrome

Two randomized, open-label, clinical trials were conducted that evaluated the efficacy and safety of GENOTROPIN in Turner syndrome patients with short stature. Turner syndrome patients were treated with GENOTROPIN alone or GENOTROPIN plus adjunctive hormonal therapy (ethinylestradiol or oxandrolone). A total of 38 patients were treated with GENOTROPIN alone in the two studies. In Study 055, 22 patients were treated for 12 months, and in Study 092, 16 patients were treated for 12 months. Patients received GENOTROPIN at a dose between 0.13 to 0.33 mg/kg/week.

SDS for height velocity and height are expressed using either the Tanner (Study 055) or Sempé (Study 092) standards for age-matched normal children as well as the Ranke standard (both studies) for age-matched, untreated Turner syndrome patients. As seen in Table 6, height velocity SDS and height SDS values were smaller at baseline and after treatment with GENOTROPIN when the normative standards were utilized as opposed to the Turner syndrome standard.

Both studies demonstrated statistically significant increases from baseline in all of the linear growth variables (i.e., mean height velocity, height velocity SDS, and height SDS) after treatment with GENOTROPIN (see Table 6). The linear growth response was greater in Study 055 wherein patients were treated with a larger dose of GENOTROPIN.

Table 6. Growth Parameters (mean ± SD) after 12 Months of Treatment with GENOTROPIN in Pediatric Patients with Turner Syndrome in Two Open Label Studies
 | GENOTROPIN 0.33 mg/kg/week Study 055^ n=22 | GENOTROPIN 0.13–0.23 mg/kg/week Study 092# n=16
Height Velocity (cm/yr)
Baseline | 4.1 ± 1.5 | 3.9 ± 1.0
Month 12 | 7.8 ± 1.6 | 6.1 ± 0.9
Change from baseline (95% CI) | 3.7 (3.0, 4.3) | 2.2 (1.5, 2.9)
Height Velocity SDS (Tanner^/Sempé# Standards) | (n=20)
Baseline | -2.3 ± 1.4 | -1.6 ± 0.6
Month 12 | 2.2 ± 2.3 | 0.7 ± 1.3
Change from baseline (95% CI) | 4.6 (3.5, 5.6) | 2.2 (1.4, 3.0)
Height Velocity SDS (Ranke Standard)
Baseline | -0.1 ± 1.2 | -0.4 ± 0.6
Month 12 | 4.2 ± 1.2 | 2.3 ± 1.2
Change from baseline (95% CI) | 4.3 (3.5, 5.0) | 2.7 (1.8, 3.5)
Height SDS (Tanner^/Sempé# Standards)
Baseline | -3.1 ± 1.0 | -3.2 ± 1.0
Month 12 | -2.7 ± 1.1 | -2.9 ± 1.0
Change from baseline (95% CI) | 0.4 (0.3, 0.6) | 0.3 (0.1, 0.4)
Height SDS (Ranke Standard)
Baseline | -0.2 ± 0.8 | -0.3 ± 0.8
Month 12 | 0.6 ± 0.9 | 0.1 ± 0.8
Change from baseline (95% CI) | 0.8 (0.7, 0.9) | 0.5 (0.4, 0.5)
SDS = Standard Deviation Score
Ranke standard based on age-matched, untreated Turner syndrome patients
Tanner^/Sempé# standards based on age-matched normal children
p<0.05, for all changes from baseline

14.5 Idiopathic Short Stature

The long-term efficacy and safety of GENOTROPIN in patients with idiopathic short stature (ISS) were evaluated in one randomized, open-label, clinical trial that enrolled 177 children. Patients were enrolled on the basis of short stature, stimulated GH secretion >10 ng/mL, and prepubertal status (criteria for idiopathic short stature were retrospectively applied and included 126 patients). All patients were observed for height progression for 12 months and were subsequently randomized to GENOTROPIN or observation only and followed to final height. Two GENOTROPIN doses were evaluated in this trial: 0.23 mg/kg/week (0.033 mg/kg/day) and 0.47 mg/kg/week (0.067 mg/kg/day). Baseline patient characteristics for the ISS patients who remained prepubertal at randomization (n= 105) were: mean (± SD): chronological age 11.4 (1.3) years, height SDS -2.4 (0.4), height velocity SDS -1.1 (0.8), and height velocity 4.4 (0.9) cm/yr, IGF-1 SDS -0.8 (1.4). Patients were treated for a median duration of 5.7 years. Results for final height SDS are displayed by treatment arm in Table 7. GENOTROPIN therapy improved final height in ISS children relative to untreated controls. The observed mean gain in final height was 9.8 cm for females and 5.0 cm for males for both doses combined compared to untreated control subjects. A height gain of 1 SDS was observed in 10% of untreated subjects, 50% of subjects receiving 0.23 mg/kg/week and 69% of subjects receiving 0.47 mg/kg/week.

Table 7. Final height SDS results for pre-pubertal patients with ISS [Mean (SD) are observed values.]
 | Untreated (n=30) | GEN 0.033 (n=30) | GEN 0.067 (n=42) | GEN 0.033 vs. Untreated (95% CI) | GEN 0.067 vs. Untreated (95% CI)
Baseline height SDS
Final height SDS minus baseline | 0.41 (0.58) | 0.95 (0.75) | 1.36 (0.64) | +0.53 (0.20, 0.87) p=0.0022 | +0.94 (0.63, 1.26) p<0.0001
Baseline predicted ht
Final height SDS minus baseline predicted final height SDS | 0.23 (0.66) | 0.73 (0.63) | 1.05 (0.83) | +0.60 (0.09, 1.11) p=0.0217 | +0.90 (0.42, 1.39) p=0.0004
**Least square means based on ANCOVA (final height SDS and final height SDS minus baseline predicted height SDS were adjusted for baseline height SDS)

16 HOW SUPPLIED/STORAGE AND HANDLING

16.1 How Supplied

GENOTROPIN (somatropin) for injection is a white, lyophilized powder in a single-patient-use or single-dose, two-chamber cartridge intended for subcutaneous injection after reconstitution. The front chamber contains somatropin and the rear chamber contains the diluent.

GENOTROPIN lyophilized powder is available in the following packages:

5 mg single‑patient‑use two-chamber cartridge (with preservative)

- After reconstitution the final concentration is 5 mg/mL
- For use with the GENOTROPIN PEN 5 Growth Hormone Delivery Device.
- Package of 1 NDC 0013-2626-81

12 mg single‑patient‑use two-chamber cartridge (with preservative)

- After reconstitution the final concentration is 12 mg/mL
- For use with the GENOTROPIN PEN 12 Growth Hormone Delivery Device.
- Package of 1 NDC 0013-2646-81

GENOTROPIN MINIQUICK, a single-dose Growth Hormone Delivery Device containing a two-chamber cartridge of GENOTROPIN (without preservative)

- After reconstitution, each GENOTROPIN MINIQUICK delivers 0.25 mL, regardless of strength.

GENOTROPIN MINIQUICK is available in the following strengths, each in a package of 7:

Strength | NDC Number
0.2 mg | NDC 0013-2649-02
0.4 mg | NDC 0013-2650-02
0.6 mg | NDC 0013-2651-02
0.8 mg | NDC 0013-2652-02
1 mg | NDC 0013-2653-02
1.2 mg | NDC 0013-2654-02
1.4 mg | NDC 0013-2655-02
1.6 mg | NDC 0013-2656-02
1.8 mg | NDC 0013-2657-02
2 mg | NDC 0013-2658-02

16.2 Storage and Handling

The 5 mg and 12 mg GENOTROPIN single-patient-use cartridges:

- Store GENOTROPIN lyophilized powder under refrigeration at 36°F to 46°F (2°C to 8°C) until the expiration date. Store in the package to protect from light. Do not freeze.
- After reconstitution, store the pen (with the cartridge) in the pen box with the pen cap on to protect from light. Store under refrigeration at 36°F to 46°F (2°C to 8°C) between each use, for up to 28 days. Do not shake. Discard the cartridge and any unused medication after 28 days. Use a GENOTROPIN PEN 5, a medical device, to reconstitute the 5 mg two-chamber cartridge, and use a GENOTROPIN PEN 12 to reconstitute the 12 mg two-chamber cartridge.

The 0.2 mg, 0.4 mg, 0.6 mg, 0.8 mg, 1.0 mg, 1.2 mg, 1.4 mg, 1.6 mg, 1.8 mg and 2 mg single-dose Growth Hormone Delivery Devices containing a two-chamber cartridge (GENOTROPIN MINIQUICK):

- Store GENOTROPIN MINIQUICK under refrigeration at 36°F to 46°F (2°C to 8°C) until the expiration date. If needed, may be stored for up to 3 months at room temperature at or below 77°F (25°C) prior to reconstitution. Do not freeze.
- After reconstitution, store GENOTROPIN MINIQUICK in the package with the pen cap on to protect from light. If needed, may be stored under refrigeration at 36°F to 46°F (2°C to 8°C) for up to 24 hours before use. Do not shake. The GENOTROPIN MINIQUICK should be used only once and then discarded.

17 PATIENT COUNSELING INFORMATION

Patients being treated with GENOTROPIN (and/or their parents) should be informed about the potential benefits and risks associated with GENOTROPIN treatment. This information is intended to better educate patients (and caregivers); it is not a disclosure of all possible adverse or intended effects.

Patients and caregivers who will administer GENOTROPIN should receive appropriate training and instruction on the proper use of GENOTROPIN from the physician or other suitably qualified health care professional. A puncture-resistant container for the disposal of used syringes and needles should be strongly recommended. Patients and/or parents should be thoroughly instructed in the importance of proper disposal, and cautioned against any reuse of needles and syringes. This information is intended to aid in the safe and effective administration of the medication.

GENOTROPIN is supplied in a two-chamber cartridge, with the lyophilized powder in the front chamber and a diluent in the rear chamber. A reconstitution device is used to mix the diluent and powder.

The GENOTROPIN 5 mg and 12 mg cartridges are color-coded to help ensure proper use with the GENOTROPIN PEN delivery device. The 5 mg cartridge has a green tip to match the green pen window on the Pen 5, while the 12 mg cartridge has a purple tip to match the purple pen window on the Pen 12.

Follow the directions for reconstitution provided with each device. Do not shake; shaking may cause denaturation of the active ingredient.

Please see accompanying directions for use of the reconstitution and/or delivery device.

Rx only

Manufactured by:
Pharmacia & Upjohn Company LLC
A subsidiary of Pfizer Inc.
New York, NY 10001
U.S. License No. 1216

This product’s labeling may have been updated. For the most recent prescribing information, please visit www.pfizer.com.

LAB-0222-26.0

Instructions for Use

GENOTROPIN 5 (JEEN-o-tro-pin 5)
GENOTROPIN PEN 5 is a medical device used to mix and inject doses of reconstituted GENOTROPIN (somatropin) for injection. Use this device only for administration of GENOTROPIN.

Important Note

Please read these instructions completely before using the GENOTROPIN PEN 5. These instructions need to be followed step by step. Please do not use the GENOTROPIN PEN 5 unless your healthcare provider has trained you.
If there is anything you do not understand or cannot do, call the Pfizer Bridge Program toll-free number at 1-800-645-1280. If you have any questions about your dose or your treatment with GENOTROPIN, call your healthcare provider.

Your pen should not be used near electrical or electronic equipment, including mobile phones. If your pen has been damaged, it should not be used and should be disposed of as instructed by your healthcare provider.

GENOTROPIN PEN 5 is a reusable multi-dose device holding a 2-chamber cartridge of GENOTROPIN, used to mix and inject GENOTROPIN during a 2 year use period.

For your injection you will need:

- 1 GENOTROPIN PEN 5 device
- 1 GENOTROPIN 5 mg single-patient-use 2-chamber cartridge
- 1 new 29 gauge (29 G), 30 gauge (30 G), or 31 gauge (31 G) Becton Dickinson pen needle
- Alcohol swab (not included)
- 1 sharps disposal container. See "Throwing away (disposing of) used needles, cartridges and your GENOTROPIN PEN 5" in Step 14.

Parts of the GENOTROPIN PEN 5 (See Figure A)

Figure A

Storage instructions for your GENOTROPIN PEN 5

- Between uses, store your pen (with the cartridge) in the refrigerator 36°F to 46°F (2°C to 8°C) in its protective case. Always remove the needle before storing.
- Do not freeze. Protect from light.
- Throw away the cartridge within 28 days after mixing, even if the cartridge is not empty.
- When travelling, keep your pen in its protective case and carry it in an insulated bag to protect it from heat or freezing. Put your pen back in the refrigerator as soon as possible.

Using your GENOTROPIN PEN 5

Step 1.

Wash your hands well with soap and water before using the GENOTROPIN PEN 5.

Step 2. Attach the Needle

- Pull off the front cap (See Figure B).

Figure B

- Unscrew the metal front part from the plastic body by turning the metal front part clockwise (to the right) (See Figure C).

Figure C

- Peel off the foil from the needle.
- Push and screw the needle onto the metal front part using the outer needle cover, by turning it counter clockwise (to the left) (See Figure D).
- Do not remove the outer needle cover and inner needle cap until you are ready to inject.

Figure D

Step 3. Insert the 2-Chamber Cartridge of GENOTROPIN
Use only the 5 mg cartridge.

- Open the cartridge pack and take out 1 cartridge.
- Check that the color on the cartridge matches the color around the window of the plastic body (See Figure E).

Figure E

- Hold the metal front part upright, and insert the cartridge. Insert the end of the cartridge with the metal cap first, as shown (See Figure F).
- Push the cartridge firmly into place.

Figure F

Step 4. Prepare your Pen

- Press the red release button. The injection button will pop up (See Figure G).

Figure G

- Turn the injection button in a counter clockwise direction (to the left) as far as it will go (See Figure H). This will draw back the plunger rod.

Figure H

- Check that the plunger rod is not visible through the plunger rod window (See Figure I). Do not proceed if the plunger rod is visible, as the medicine will not be properly mixed.

Figure I

Step 5. Mix your GENOTROPIN

- Make sure that a needle is attached to the metal front part.
- While holding your pen upright, gently screw the metal front part and the plastic body back together as shown (See Figure J). Make sure that the metal front part is firmly attached to the plastic body. This mixes the liquid and the powder.

Figure J

Step 6. Examine the Solution

- Gently tip your pen from side to side to help dissolve the powder completely (See Figure K).

Figure K

- Do not shake your pen, as this might stop the growth hormone from working. Check that the solution (combined growth hormone powder and liquid) is clear in the cartridge window (See Figure L).
- If you see particles, or if the solution is not clear, do not inject. Remove the cartridge and use a new one.

Figure L

Step 7. Release Trapped Air

- Remove both the outer needle cover and inner needle cap. Throw away (dispose of) both the inner needle cap and outer needle cover. Do not to touch the exposed needle.

- Remove any trapped air from the solution as follows:

  a) Turn the injection button so that the white mark on the injection button lines up with the black mark on the plastic body (See Figure M).

Figure M

  b) Hold your pen with the needle pointing upwards. Gently tap the metal front part with your finger to move any air bubbles to the top.

  c) Push the injection button all the way in. You will see a drop of liquid appear at the needle tip. Any trapped air has now been released (See Figure N).

Figure N

  d) If you do not see liquid at the needle tip, press the red release button. Then turn the injection button in the direction of the arrow until it clicks 1 time, and the dose display shows '0.1'. Repeat steps b) and c) to remove any trapped air from the solution (see Figure O).

Figure O

Step 8. Attach the Needle Guard (Optional)
The needle guard is intended to hide the needle before, during and after injection and to reduce needle injury. You can choose to use the needle guard, if desired.

- Grip the sides of the needle guard. Push it over the needle until it snaps in place (See Figure P). Do not push the needle guard on the end.
  Be careful not to touch the exposed needle.

Figure P

My daily dose is mg (write in your daily dose)

Step 9. Dial Your Prescribed Dose

- Press the red release button to reset your pen.
- The button will pop up and the dose display window will read '0.0'.
- Turn the injection button in a clockwise direction (to the right) as shown, until your prescribed dose is displayed (See Figure Q).
- If you turn the button too far, turn it back the other way until your correct dose is displayed.

Figure Q

Step 10. Inject your GENOTROPIN

- Choose an injection site (thigh, buttocks, or abdomen) as recommended by your healthcare provider. Choose a different site each time you give yourself an injection. Each new injection should be given at least 1 inch from the site you used before (see Figure R).
- Avoid areas that are bony, bruised, red, sore or hard. You should also avoid areas of the skin that have scars or skin problems.
- Clean the injection site with the alcohol swab.
- Allow the injection site to dry.

Figure R

- Firmly pinch a fold of skin at the injection area. Push the needle fully into the skin fold at a 90° angle as shown (See Figure S).
- Push the injection button until it clicks. Wait while counting slowly for 5 seconds, and then remove the needle from the skin. This is to make sure that the entire dose has been injected (See Figure S).

Figure S

Step 11. Throw away the Needle and Store your GENOTROPIN PEN 5

- Pull off the needle guard, gripping the sides. Be careful not to push on the end. (See Figure T).
- Remove the needle as instructed by your healthcare provider, and throw it away in a sharps disposal container (See Step 14). Do not reuse the needle.
- Push on the front cap, and put your pen back in its protective case.
- Store your pen (with the cartridge) in the refrigerator between 36ºF to 46ºF (2ºC to 8ºC) until your next injection.

Figure T

Step 12. Your Next Injection
If you already have a cartridge in your pen, prepare the pen and give the injection as follows:

- Remove the front cap (See Figure U).

Figure U

- Make sure there is enough growth hormone solution in the cartridge for your dose. Check the position of the plunger against the indicative scale in the cartridge window (See Figure V).
- Peel off the foil from a needle.

Figure V

- Push and screw the needle onto the metal front part of the pen as shown (See Figure W). Remove the outer needle cover and inner needle cap.
- Follow the instructions above, starting with Step 8: Attach the Needle Guard.

Figure W

Step 13. To Replace the Cartridge

- Press the red release button to reset your pen (See Figure X).

Figure X

- Turn the injection button in a counter clockwise direction (to the left) as far as it will go as shown (See Figure Y).This will draw back the plunger rod.

Figure Y

- Unscrew the metal front part and remove the empty cartridge (See Figure Z).
- Throw away the empty cartridge as instructed by your healthcare provider.
- To insert a new cartridge and prepare your pen for reuse, follow the instructions starting with Step 1.

Figure Z

Step 14. Throwing away (disposing of) used needles, cartridges and your GENOTROPIN PEN 5
Put the used needles and cartridges in a FDA-cleared sharps disposal container right away after use. Do not throw away (dispose of) the needles and cartridges in the household trash.

If you do not have a FDA-cleared sharps disposal container, you may use a household container that is:

- Made of a heavy-duty plastic,
- Can be closed with a tight fitting, puncture-resistant lid, without sharps being able to come out,
- Upright and stable during use,
- Leak-resistant, and
- Properly labeled to warn of hazardous waste inside the container.

When your sharps disposal container is almost full, you will need to follow your community guidelines for the right way to dispose of your sharps disposal container. There may be state or local laws about how you should throw away used needles and cartridges. For more information about safe sharps disposal, and for specific information about sharps disposal in the state that you live in, go to the FDA's website at: http://www.fda.gov/safesharpsdisposal.

- Do not reuse needles.
- Do not throw away (dispose of) your used sharps disposal container in your household trash unless your community guidelines permit this.
- Do not recycle your used sharps disposal container.

Important: Always keep the sharps disposal container out of the reach of children.

Dispose of the entire GENOTROPIN PEN 5 as electronic waste per state and local regulations.

Customizing your Pen

Your pen is supplied with 2 colored clip-on panels, so that you can customize the look of your pen. To remove the clip-on panel from the pen, insert the lip of the front cap into the groove under the front end of the panel, and pry the panel off. The new panel simply clicks into place (See Figure AA).

Figure AA

Caring for your Pen
To clean your pen, wipe the outside surface with a damp cloth. Do not put the pen in water or this may damage your pen. Do not use alcohol or any other cleaning agents to clean the pen, as they may damage the plastic body. To clean the needle guard, wipe it with a damp cloth or alcohol pad.

Questions and Answers
Question | Answer
How long is the use period of my pen? | The pen has a use period of 2 years starting from the first use by the patient.
How can I tell how much GENOTROPIN is left in my pen? | The indicative scale along the side of the cartridge window is a guide. The number that aligns with the front edge of the rubber stopper shows you how many milligrams are left in the cartridge. If your cartridge is nearly empty you can also dial the injection button until it cannot go any further. The dose display will then show the maximum dose that can be delivered. When the cartridge is empty, the injection button will not turn any further.
If the display does not work, can my pen still be used? | Contact your healthcare provider as soon as possible to get a new pen.
What happens if I dial the injection button beyond the maximum dose ('2.0' mg)? | Some liquid may appear from the needle tip, and the numbers may disappear from the dose display. This is normal and will not affect your injection. To correct this, turn the injection button in the opposite direction of the arrow until numbers reappear on the dose display. Then dial back to your correct dose.
Why is it difficult to turn or push the injection button? | The injection button may become difficult to turn or to push. This may occur if the pen gets dirty due to contact with food, liquids or GENOTROPIN, or if the needle becomes clogged. Contact your healthcare provider if the issue does not resolve.

Display Information:

 | Steady |  | The selected dose size. The number indicates the dose size (in mg) that your pen will deliver if the injection button is fully pressed in.
 | Steady |  | A dose is not set. The injection button has been turned too far in the opposite direction to the arrow on the injection button while setting the dose.
 | Flashing |  | The injection button is rotated too fast or too slow. Point your pen away from your face, press the injection button, press the red release button and continue preparing your dose.
 | Flashing |  | The injection button is rotated too fast or too slow. Point your pen away from your face, press the injection button, press the red release button and continue preparing your dose.
 | Flashing |  | 1 month before the end of the 2 year use period.
 | (5 seconds) |  | This is normal. The dose can be set and read from the display. Contact your healthcare provider as soon as possible to get a new Pen.
 | Steady |  | Pen has reached the end of its use period of 2 years.
 |  |  | The display will continue to show until the battery is completely empty. This does not indicate a problem with the pen. Your pen can still be used correctly, but the dose size will not be displayed. Contact your healthcare provider right away to get a new Pen.
 | Flashing |  | Battery charge is low and will be empty in 1 month. Afterwards the dose can be set and your pen can be used correctly. Contact your healthcare provider as soon as possible to get a new Pen.
 | (5 seconds) |  | Battery charge is low and will be empty in 1 month. Afterwards the dose can be set and your pen can be used correctly. Contact your healthcare provider as soon as possible to get a new Pen.
 | Steady |  | Battery power low. The dose cannot be displayed. Contact your healthcare provider right away to get a new Pen.
 | Steady |  | Blank screen To save the battery energy, the dose display is activated for 2 minutes and then automatically disappears. Although the display is no longer visible, the dose remains available for delivery

If you have any questions about your dose or your treatment with GENOTROPIN, call your healthcare provider right away.

Use this device only for the person for whom it was prescribed.

This Instructions for Use has been approved by the U.S. Food and Drug Administration.

Caution: Federal law restricts this device to sale by or on the order of a physician.

Manufactured by:

Pharmacia & Upjohn Company LLC

A subsidiary of Pfizer Inc.

New York, NY 10001

U.S. License No. 1216

LAB-0225-10.0

Revised August 2024

INSTRUCTIONS FOR USE
GENOTROPIN 12 (JEEN-o-tro-pin 12)
GENOTROPIN PEN 12 is a medical device used to mix and inject doses of reconstituted GENOTROPIN (somatropin) for injection. Use this device only for administration of GENOTROPIN.

Important Note

Please read these instructions completely before using the GENOTROPIN PEN 12. These instructions need to be followed step by step. Please do not use the GENOTROPIN PEN 12 unless your healthcare provider has trained you. If there is anything you do not understand or cannot do, call the Pfizer Bridge Program toll-free number at 1-800-645-1280. If you have any questions about your dose or your treatment with GENOTROPIN, call your healthcare provider.

Your pen should not be used near electrical or electronic equipment, including mobile phones. If your pen has been damaged, it should not be used and should be disposed of as instructed by your healthcare provider.

GENOTROPIN PEN 12 is a reusable multi-dose device holding a 2-chamber cartridge of GENOTROPIN, used to mix and inject GENOTROPIN during a 2 year use period.

For your injection you will need:

- 1 GENOTROPIN PEN 12 device
- 1 GENOTROPIN 12 mg single-patient-use 2-chamber cartridge
- 1 new 29 gauge (29 G), 30 gauge (30 G), or 31 gauge (31 G) Becton Dickinson pen needle
- Alcohol swab (not included)
- 1 sharps disposal container. See "Throwing away (disposing of) used needles, cartridges and your GENOTROPIN PEN 12" in Step 14.

Parts of the GENOTROPIN PEN 12 (See Figure A)

Figure A

Storage instructions for your GENOTROPIN PEN 12

- Between uses, store your pen (with the cartridge) in the refrigerator between 36°F to 46°F (2°C to 8°C) in its protective case. Always remove the needle before storing.
- Do not freeze. Protect from light.
- Throw away the cartridge within 28 days after mixing, even if the cartridge is not empty.
- When travelling, keep your pen in its protective case and carry it in an insulated bag to protect it from heat or freezing. Put your pen back in the refrigerator as soon as possible.

Using your GENOTROPIN PEN 12

Step 1.
Wash your hands well with soap and water before using the GENOTROPIN PEN 12.

Step 2. Attach the Needle

- Pull off the front cap (See Figure B).

Figure B

- Unscrew the metal front part from the plastic body by turning the metal front part clockwise (to the right) (See Figure C).

Figure C

- Peel off the foil from the needle.
- Push and screw the needle onto the metal front part using the outer needle cover, by turning it counter clockwise (to the left) (See Figure D).
- Do not remove the outer needle cover and inner needle cap until you are ready to inject.

Figure D

Step 3. Insert the 2-Chamber Cartridge of GENOTROPIN
Use only the 12 mg cartridge.

- Open the cartridge pack and take out 1 cartridge.
- Check that the color on the cartridge matches the color around the window of the plastic body (See Figure E).

Figure E

- Hold the metal front part upright, and insert the cartridge. Insert the end of the cartridge with the metal cap first, as shown (See Figure F).
- Push the cartridge firmly into place.

Figure F

Step 4. Prepare the Pen

- Press the red release button. The injection button will pop up (See Figure G).

Figure G

- Turn the injection button in a counter clockwise direction (to the left) as far as it will go (See Figure H). This will draw back the plunger rod.

Figure H

- Check that the plunger rod is not visible through the plunger rod window (See Figure I). Do not proceed if the plunger rod is visible, as the medicine will not be properly mixed.

Figure I

Step 5. Mix your GENOTROPIN

- Make sure that a needle is attached to the metal front part.
- While holding your pen upright, gently screw the metal front part and the plastic body back together as shown (See Figure J). Make sure that the metal front part is firmly attached to the plastic body. This mixes the liquid and the powder.

Figure J

Step 6. Examine the Solution

- Gently tip the pen from side to side to help dissolve the powder completely (See Figure K).

Figure K

- Do not shake your pen, as this might stop the growth hormone from working. Check that the solution (combined growth hormone powder and liquid) is clear in the cartridge window (See Figure L).

If you see particles, or if the solution is not clear, do not inject. Remove the cartridge and use a new one.

Figure L

Step 7. Release Trapped Air

- Remove both the outer needle cover and inner needle cap. Throw away (dispose of) both the inner needle cap and outer needle cover. Do not touch the exposed needle.

- Remove any trapped air from the solution as follows:

  a) Turn the injection button so that the white mark on the injection button lines up with the black mark on the plastic body (See Figure M).

Figure M

  b) Hold your pen with the needle pointing upwards (See Figure N). Gently tap the metal front part with your finger to move any air bubbles to the top.

Figure N

  c) Push the injection button all the way in. You will see a drop of liquid appear at the needle tip. Any trapped air has now been released (See Figure N).

  d) If you do not see liquid at the needle tip, press the red release button. Then turn the injection button in the direction of the arrow until it clicks 1 time, and the dose display shows '0.2'. Repeat steps b) and c) to remove any trapped air from the solution (See Figure O).

Figure O

Step 8. Attach the Needle Guard (Optional)
The needle guard is intended to hide the needle before, during and after injection and to reduce needle injury. You can choose to use the needle guard, if desired.

- Grip the sides of the needle guard. Push it over the needle until it snaps in place (See Figure P). Do not push the needle guard on the end.

Be careful not to touch the exposed needle.

Figure P

My daily dose is mg (write in your daily dose)

Step 9. Dial Your Prescribed Dose

- Press the red release button to reset your pen.
- The button will pop up and the dose display window will read '0.0'.
- Turn the injection button in a clockwise direction (to the right) as shown until your prescribed dose is displayed (See Figure Q).
- If you turn the button too far, turn it back the other way until your correct dose is displayed.

Figure Q

Step 10. Inject your GENOTROPIN

- Choose an injection site (thigh, buttocks, or abdomen) as recommended by your healthcare provider. Choose a different site each time you give yourself an injection. Each new injection should be given at least 1 inch from the site you used before (See Figure R).
- Avoid areas that are bony, bruised, red, sore or hard, and areas of the skin that have scars or skin conditions.
- Clean the injection site with the alcohol swab.
- Allow the injection site to dry.

Figure R

- Firmly pinch a fold of skin at the injection area. Push the needle fully into the skin fold at a 90° angle as shown (See Figure S).
- Push the injection button until it clicks. Wait while counting slowly for 5 seconds, and then remove the needle from the skin. This is to make sure that the entire dose has been injected (See Figure S).

Figure S

Step 11. Throw away the Needle and Store the GENOTROPIN PEN 12

- Pull off the needle guard, gripping the sides. Be careful not to push on the end (See Figure T).
- Remove the needle as instructed by your healthcare provider, and throw it away in a sharps disposal container (See Step 14). Do not reuse the needle.
- Push on the front cap, and put your pen back in its protective case.
- Store your pen (with the cartridge) in the refrigerator between 36°F to 46°F (2°C to 8°C) until your next injection.

Figure T

Step 12. Your Next Injection
If you already have a cartridge in your pen, prepare the pen and give the injection as follows:

- Remove the front cap (See Figure U).

Figure U

- Make sure there is enough growth hormone solution in the cartridge for your dose. Check the position of the plunger against the indicative scale in the cartridge window (See Figure V).
- Peel off the foil from a needle.

Figure V

- Push and screw the needle onto the metal front part of your pen as shown (See Figure W). Remove the outer needle cover and inner needle cap.
- Follow the instructions above, starting with Step 8: Attach the Needle Guard.

Figure W

Step 13. To Replace the Cartridge

- Press the red release button to reset your pen (See Figure X).

Figure X

- Turn the injection button in a counter clockwise direction (to the left) as far as it will go as shown (See Figure Y). This will draw back the plunger rod.

Figure Y

- Unscrew the metal front part and remove the empty cartridge (See Figure Z).
- Throw away the empty cartridge as instructed by your healthcare provider.
- To insert a new cartridge and prepare your pen for reuse, follow the instructions starting with Step 1.

Figure Z

Step 14. Throwing away (disposing of) used needles, cartridges and your GENOTROPIN PEN 12
Put the used needles and cartridges in a FDA-cleared sharps disposal container right away after use. Do not throw away (dispose of) the needles and cartridges in the household trash.

If you do not have a FDA-cleared sharps disposal container, you may use a household container that is:

- Made of a heavy-duty plastic,
- Can be closed with a tight fitting, puncture-resistant lid, without sharps being able to come out,
- Upright and stable during use,
- Leak-resistant, and
- Properly labeled to warn of hazardous waste inside the container.

When your sharps disposal container is almost full, you will need to follow your community guidelines for the right way to dispose of your sharps disposal container. There may be state or local laws about how you should throw away used needles and cartridges. For more information about safe sharps disposal, and for specific information about sharps disposal in the state that you live in, go to the FDA's website at: http://www.fda.gov/safesharpsdisposal.

- Do not reuse needles.
- Do not throw away (dispose of) your used sharps disposal container in your household trash unless your community guidelines permit this.
- Do not recycle your used sharps disposal container.

Important: Always keep the sharps disposal container out of the reach of children.

Dispose of the entire GENOTROPIN PEN 12 as electronic waste per state and local regulations.

Customizing your Pen
Your pen is supplied with 2 colored clip-on panels, so that you can customize the look of your pen. To remove the clip-on panel from your pen, insert the lip of the front cap into the groove under the front end of the panel, and pry the panel off. The new panel simply clicks into place (See Figure AA).

Figure AA

Caring for your Pen

To clean your pen, wipe the outside surface with a damp cloth. Do not put the pen in water as this may damage your pen. Do not use alcohol or any other cleaning agents to clean the pen, as they may damage the plastic body. To clean the needle guard, wipe it with a damp cloth or alcohol pad.

Questions and Answers
Question | Answer
How long is the use period of my pen? | The pen has a use period of 2 years starting from the first use by the patient.
How can I tell how much GENOTROPIN is left in my pen? | The indicative scale along the side of the cartridge window is a guide. The number that aligns with the front edge of the rubber stopper shows you how many milligrams are left in the cartridge. If your cartridge is nearly empty you can also dial the injection button until it cannot go any further, the dose display will then show the maximum dose that can be delivered. When the cartridge is empty, the injection button will not turn any further.
If the display does not work, can my pen still be used? | Contact your healthcare provider as soon as possible to get a new pen.
What happens if I dial the injection button beyond the maximum dose ('4.0' mg)? | Some liquid may appear from the needle tip, and the numbers may disappear from the dose display. This is normal and will not affect your injection. To correct this, turn the injection button in the opposite direction of the arrow until numbers reappear on the dose display. Then dial back to your correct dose.
Why is it difficult to turn or push the injection button? | The injection button may become difficult to turn or to push. This may occur if the pen gets dirty due to contact with food, liquids or GENOTROPIN, or if the needle becomes clogged. Contact your healthcare provider if the issue does not resolve.

Display Information

 | Steady |  | The selected dose size. The number indicates the dose size (in mg) that your pen will deliver if the injection button is fully pressed in.
 | Steady |  | A dose is not set. The injection button has been turned too far in the opposite direction to the arrow on the injection button while setting the dose.
 | Flashing |  | The injection button is rotated too fast or too slow. Point the pen away from your face, press the injection button, press the red release button and continue preparing your dose.
 | Flashing |  | The injection button is rotated too fast or too slow. Point the pen away from your face, press the injection button, press the red release button and continue preparing your dose.
 | Flashing |  | 1 month before the end of the 2 year use period.
 | (5 seconds) |  | This is normal. The dose can be set and read from the display. Contact your healthcare provider as soon as possible to get a new Pen.
 | Steady |  | Pen has reached the end of its use period of 2 years.
 |  |  | The display will continue to show until the battery is completely empty. This does not indicate a problem with your pen. Your pen can still be used correctly, but the dose size will not be displayed. Contact your healthcare provider right away to get a new Pen.
 | Flashing |  | Battery charge is low and will be empty in 1 month.
 | (5 seconds) |  | Afterwards the dose can be set and your pen can be used correctly. Contact your healthcare provider as soon as possible to get a new Pen.
 | Steady |  | Battery power low. The dose cannot be displayed. Contact your healthcare provider right away to get a new Pen.
 | Steady |  | Blank screen To save the battery energy, the dose display is activated for 2 minutes and then automatically disappears. Although the display is no longer visible, the dose remains available for delivery.

If you have any questions about your dose or your treatment with GENOTROPIN, call your healthcare provider right away.

Use this device only for the person for whom it was prescribed.

This Instructions for Use has been approved by the U.S. Food and Drug Administration.
Caution: Federal law restricts this device to sale by or on the order of a physician.

Manufactured by:
Pharmacia & Upjohn Company LLC
A subsidiary of Pfizer Inc.
New York, NY 10001
U.S. License No. 1216

LAB-0224-10.0

Revised August 2024

INSTRUCTIONS FOR USE
GENOTROPIN MINIQUICK (JEEN-o-tro-pin MIN-ee-kwik)
Growth Hormone Delivery Device containing GENOTROPIN® (somatropin) for injection

Important Note

Please read these instructions completely before using GENOTROPIN MINIQUICK. If there is anything you do not understand or cannot do, call the Pfizer Bridge Program toll-free number at 1-800-645-1280.

GENOTROPIN MINIQUICK is available in 10 dose strengths. Check your GENOTROPIN MINIQUICK to be sure you have the dose your healthcare provider prescribed.

GENOTROPIN MINIQUICK is a device holding a 2-chamber cartridge of GENOTROPIN, used to mix and inject a single dose of GENOTROPIN.

For each injection you will need:

- 2 alcohol pads (not included)
- 1 GENOTROPIN MINIQUICK device with the single‑dose 2-chamber cartridge of GENOTROPIN inside. The 2-chamber cartridge of GENOTROPIN contains the growth hormone powder in one chamber and the liquid in the other.
- 1 injection needle. A needle for injection is provided with each device. If you need additional needles, ask your healthcare provider for a 29 gauge (29 G), 30 gauge (30 G), or 31 gauge (31 G) Becton Dickinson pen needle.
- 1 sharps disposal container (not included). See "Throwing away (disposing of) your GENOTROPIN MINIQUICK and needles" in Step 12.

Parts of the GENOTROPIN MINIQUICK (See Figure A)

Storage instructions for your GENOTROPIN MINIQUICK

- Keep your GENOTROPIN MINIQUICK in the original carton to protect it from light.
- Before you mix the growth hormone powder with the liquid in the syringe, you can store the GENOTROPIN MINIQUICK in the refrigerator between 36ºF to 46ºF (2ºC to 8ºC). You can also store the GENOTROPIN MINIQUICK at room temperature between 68ºF to 77ºF (20ºC to 25ºC) for up to 3 months. Do not freeze.
- Inject the GENOTROPIN right after you mix it. If that is not possible, you can keep the GENOTROPIN MINIQUICK in the refrigerator between 36ºF to 46ºF (2ºC to 8ºC) for up to 24 hours after mixing it. Do not freeze.

Using your GENOTROPIN MINIQUICK

Step 1.
Wash your hands well with soap and water before using the GENOTROPIN MINIQUICK.

Step 2.
Open the plastic bag that contains your GENOTROPIN MINIQUICK by tearing the bag along the dotted lines on the plastic.

Step 3.
Wipe the rubber stopper on the GENOTROPIN MINIQUICK with an alcohol pad. (See Figure B)

Figure B

Step 4.
Peel the seal from the back of the injection needle. Leave both the inner needle cover and the outer needle cover on the needle. (See Figure C)

Figure C

Step 5.

- Attach the needle onto the GENOTROPIN MINIQUICK by pushing it down and turning it clockwise (to the right) until it will no longer turn.
- Make sure the needle is placed directly over the rubber stopper (not at an angle), before screwing the needle onto the rubber stopper of the GENOTROPIN MINIQUICK. (See Figure D)

Figure D

Step 6.

- Hold the GENOTROPIN MINIQUICK with the needle pointing up. Turn the plunger rod clockwise (to the right) until it will not go any further. (See Figure E) This will automatically mix the growth hormone powder and the liquid.
- Do not shake the GENOTROPIN MINIQUICK. Shaking may cause the growth hormone to not work as well.
- Make sure the solution (combined growth hormone powder and liquid) is clear, and that the growth hormone powder is completely dissolved. If you see particles in the solution, or if the solution is discolored, do not inject it. Call the Pfizer Bridge Program at 1-800-645-1280.

Figure E

Step 7.

- Choose an injection site (thigh, buttocks, or abdomen) as recommended by your healthcare provider. Choose a different site each time you give yourself an injection. Each new injection should be at least 1 inch from the site you used before (See Figure F).
  Avoid areas that are bony, bruised, red, sore or hard. You should also avoid areas that have scars or skin problems.
- Clean the injection site with the alcohol swab. Allow the injection site to dry.

Figure F

Step 8.

- Remove the outer needle cover and the inner needle cover from the needle. Save the outer needle cover. (See Figure G)

Figure G

Step 9.

- Pinch a fold of skin at the injection site firmly, and push the needle straight into the skin at a 90°angle. (See Figure H)

Figure H

Step 10.

- Push the plunger rod in as far as it will go, to inject all of the medicine in the GENOTROPIN MINIQUICK into the fold of skin. (See Figure I)
- Wait a few seconds to be sure that all of the growth hormone solution has been injected. Pull out the needle.

Figure I

Step 11

- Replace the outer needle cover on the needle. (See Figure J)

Figure J

Step 12. Throwing away (disposing of) your GENOTROPIN MINIQUICK and needles

Put the used GENOTROPIN MINIQUICK and needles in a FDA-cleared sharps disposal container right away after use. Do not throw away (dispose of) the needles and syringes in the household trash.

If you do not have a FDA-cleared sharps disposal container, you may use a household container that is:

- Made of a heavy-duty plastic,
- Can be closed with a tight fitting, puncture-resistant lid, without sharps being able to come out,
- Upright and stable during use,
- Leak-resistant, and
- Properly labeled to warn of hazardous waste inside the container.

When your sharps disposal container is almost full, you will need to follow your community guidelines for the right way to dispose of your sharps disposal container. There may be state or local laws about how you should throw away used needles and syringes. For more information about safe sharps disposal, and for specific information about sharps disposal in the state that you live in, go to the FDA's website at: http://www.fda.gov/safesharpsdisposal.

- Do not reuse the GENOTROPIN MINIQUICK or needles.
- Do not throw away (dispose of) your used sharps disposal container in your household trash unless your community guidelines permit this.
- Do not recycle your used sharps disposal container.

Important: Always keep the sharps disposal container out of the reach of children.

Questions and Answers
Question | Answer
Is it a problem if I see air bubbles in the syringe? | No. There is no need to remove the air bubbles from the GENOTROPIN MINIQUICK. The small amount of air in the syringe does not affect your injection.
What should I do if I have problems turning the plunger rod (Step 6)? | The problem could be because the needle has been inserted at an angle onto the rubber stopper. Carefully replace the outer needle cover on the needle and unscrew counterclockwise (turn to the left) to remove the needle. Hold the GENOTROPIN MINIQUICK with the needle-end pointing up, and re-attach and screw the needle directly (not at an angle) on top of the device.
What should I do if I have problems pushing the plunger when making the injection (Step 10)? | The problem could be because the needle has been inserted at an angle onto the rubber stopper. Carefully replace the outer needle cover on the needle and unscrew counterclockwise (turn to the left) to remove the needle. Hold the GENOTROPIN MINIQUICK with the needle-end pointing up, and re-attach and screw the needle directly (not at an angle) on top of the device.
What should I do if the needle is damaged or bent? | Throw away the needle and use a new needle with the GENOTROPIN MINIQUICK. See "Disposing of (throwing away) your GENOTROPIN MINIQUICK and needles".

If you have any questions about your dose or your treatment with GENOTROPIN, call your healthcare provider right away.

Use this device only for the person for whom it was prescribed.

This Instructions for Use has been approved by the U.S. Food and Drug Administration.

Manufactured by:
Pharmacia & Upjohn Company LLC
A subsidiary of Pfizer Inc.
New York, NY 10001
U.S. License No. 1216

LAB-0227-9.0
Revised: August 2024

PRINCIPAL DISPLAY PANEL - 5 mg Cartridge Label

Genotropin®
(somatropin) for injection
Two-chamber cartridge
For s.c. injection. 5 mg/mL
Refrigerate. Protect from light.
Pharmacia & Upjohn Co
Div of Pfizer Inc, NY, NY 10017

5 mg

NDC 0013-2626-81

LOT/EXP
PAA185891

PRINCIPAL DISPLAY PANEL - 5 mg Kit Carton

Pfizer
Genotropin®
5 mg

(somatropin) for injection
NDC 0013-2626-81

For subcutaneous injection
Rx only
1 Two-Chamber Cartridge

PAA185820

OPEN HERE

PRINCIPAL DISPLAY PANEL - 12 mg Cartridge Label

Genotropin®
(somatropin) for injection
Two-chamber cartridge
For s.c. injection. 12 mg/mL
Refrigerate. Protect from light.
Pharmacia & Upjohn Co
Div of Pfizer Inc, NY, NY 10017

12 mg

NDC 0013-2646-81

LOT/EXP
PAA185895

PRINCIPAL DISPLAY PANEL - 12 mg Kit Carton

Pfizer
Genotropin®
12 mg

(somatropin) for injection
NDC 0013-2646-81

For subcutaneous injection
Rx only
1 Two-Chamber Cartridge

PAA185893

OPEN HERE

PRINCIPAL DISPLAY PANEL - 0.2 mg Cartridge Label

Genotropin®
(somatropin) for injection
Genotropin MiniQuick®
Growth Hormone Delivery Device
Pharmacia & Upjohn Co
Div of Pfizer Inc, NY, NY 10017

0.2 mg

NDC 0013-2649-01

PAA142719

LOT
EXP

PRINCIPAL DISPLAY PANEL - 0.2 mg Kit Carton

NDC 0013-2649-02

Pfizer

Genotropin®
(somatropin) for injection

0.2 mg Genotropin MiniQuick®

For single subcutaneous injection only
Growth Hormone Delivery Device

Rx only

7 Pack

PRINCIPAL DISPLAY PANEL - 0.4 mg Cartridge Label

Genotropin®
(somatropin) for injection
Genotropin MiniQuick®
Growth Hormone Delivery Device
Pharmacia & Upjohn Co
Div of Pfizer Inc, NY, NY 10017

0.4 mg

NDC 0013-2650-01

PAA142720

LOT
EXP

PRINCIPAL DISPLAY PANEL - 0.4 mg Kit Carton

NDC 0013-2650-02

Pfizer

Genotropin®
(somatropin) for injection

0.4 mg Genotropin MiniQuick®

For single subcutaneous injection only
Growth Hormone Delivery Device

Rx only

7 Pack

PRINCIPAL DISPLAY PANEL - 0.6 mg Cartridge Label

Genotropin®
(somatropin) for injection
Genotropin MiniQuick®
Growth Hormone Delivery Device
Pharmacia & Upjohn Co
Div of Pfizer Inc, NY, NY 10017

0.6 mg

NDC 0013-2651-01

PAA142731

LOT
EXP

PRINCIPAL DISPLAY PANEL - 0.6 mg Kit Carton

NDC 0013-2651-02

Pfizer

Genotropin®
(somatropin) for injection

0.6 mg Genotropin MiniQuick®

For single subcutaneous injection only
Growth Hormone Delivery Device

Rx only

7 Pack

PRINCIPAL DISPLAY PANEL - 0.8 mg Cartridge Label

Genotropin®
(somatropin) for injection
Genotropin MiniQuick®
Growth Hormone Delivery Device
Pharmacia & Upjohn Co
Div of Pfizer Inc, NY, NY 10017

0.8 mg

NDC 0013-2652-01

PAA142732

LOT
EXP

PRINCIPAL DISPLAY PANEL - 0.8 mg Kit Carton

NDC 0013-2652-02

Pfizer

Genotropin®
(somatropin) for injection

0.8 mg Genotropin MiniQuick®

For single subcutaneous injection only
Growth Hormone Delivery Device

Rx only

7 Pack

PRINCIPAL DISPLAY PANEL - 1 mg Cartridge Label

Genotropin®
(somatropin) for injection
Genotropin MiniQuick®
Growth Hormone Delivery Device
Pharmacia & Upjohn Co
Div of Pfizer Inc, NY, NY 10017

1 mg

NDC 0013-2653-01

PAA142733

LOT
EXP

PRINCIPAL DISPLAY PANEL - 1 mg Kit Carton

NDC 0013-2653-02

Pfizer

Genotropin®
(somatropin) for injection

1 mg Genotropin MiniQuick®

For single subcutaneous injection only
Growth Hormone Delivery Device

Rx only

7 Pack

PRINCIPAL DISPLAY PANEL - 1.2 mg Cartridge Label

Genotropin®
(somatropin) for injection
Genotropin MiniQuick®
Growth Hormone Delivery Device
Pharmacia & Upjohn Co
Div of Pfizer Inc, NY, NY 10017

1.2 mg

NDC 0013-2654-01

PAA142734

LOT
EXP

PRINCIPAL DISPLAY PANEL - 1.2 mg Kit Carton

NDC 0013-2654-02

Pfizer

Genotropin®
(somatropin) for injection

1.2 mg Genotropin MiniQuick®

For single subcutaneous injection only
Growth Hormone Delivery Device

Rx only

7 Pack

PRINCIPAL DISPLAY PANEL - 1.4 mg Cartridge Label

Genotropin®
(somatropin) for injection
Genotropin MiniQuick®
Growth Hormone Delivery Device
Pharmacia & Upjohn Co
Div of Pfizer Inc, NY, NY 10017

1.4 mg

NDC 0013-2655-01

PAA142735

LOT
EXP

PRINCIPAL DISPLAY PANEL - 1.4 mg Kit Carton

NDC 0013-2655-02

Pfizer

Genotropin®
(somatropin) for injection

1.4 mg Genotropin MiniQuick®

For single subcutaneous injection only
Growth Hormone Delivery Device

Rx only

7 Pack

PRINCIPAL DISPLAY PANEL - 1.6 mg Cartridge Label

Genotropin®
(somatropin) for injection
Genotropin MiniQuick®
Growth Hormone Delivery Device
Pharmacia & Upjohn Co
Div of Pfizer Inc, NY, NY 10017

1.6 mg

NDC 0013-2656-01

PAA142736

LOT
EXP

PRINCIPAL DISPLAY PANEL - 1.6 mg Kit Carton

NDC 0013-2656-02

Pfizer

Genotropin®
(somatropin) for injection

1.6 mg Genotropin MiniQuick®

For single subcutaneous injection only
Growth Hormone Delivery Device

Rx only

7 Pack

PRINCIPAL DISPLAY PANEL - 1.8 mg Cartridge Label

Genotropin®
(somatropin) for injection
Genotropin MiniQuick®
Growth Hormone Delivery Device
Pharmacia & Upjohn Co
Div of Pfizer Inc, NY, NY 10017

1.8 mg

NDC 0013-2657-01

PAA142737

LOT
EXP

PRINCIPAL DISPLAY PANEL - 1.8 mg Kit Carton

NDC 0013-2657-02

Pfizer

Genotropin®
(somatropin) for injection

1.8 mg Genotropin MiniQuick®

For single subcutaneous injection only
Growth Hormone Delivery Device

Rx only

7 Pack

PRINCIPAL DISPLAY PANEL - 2 mg Cartridge Label

Genotropin®
(somatropin) for injection
Genotropin MiniQuick®
Growth Hormone Delivery Device
Pharmacia & Upjohn Co
Div of Pfizer Inc, NY, NY 10017

2 mg

NDC 0013-2658-01

PAA142738

LOT
EXP

PRINCIPAL DISPLAY PANEL - 2 mg Kit Carton

NDC 0013-2658-02

Pfizer

Genotropin®
(somatropin) for injection

2 mg Genotropin MiniQuick®

For single subcutaneous injection only
Growth Hormone Delivery Device

Rx only

7 Pack